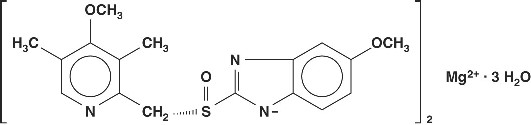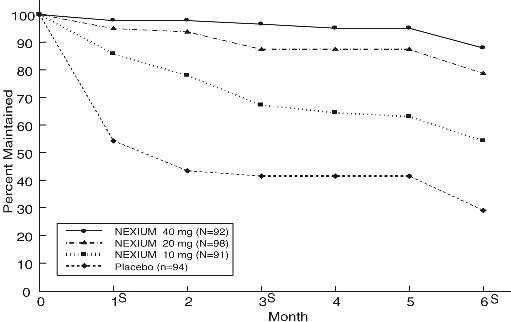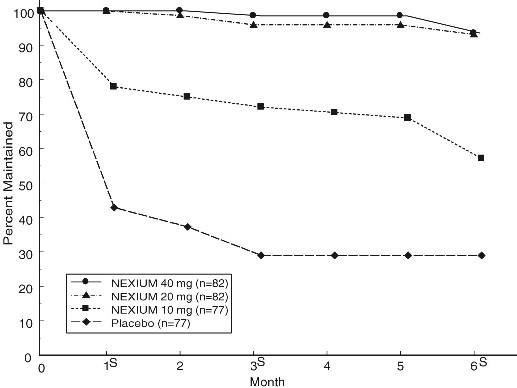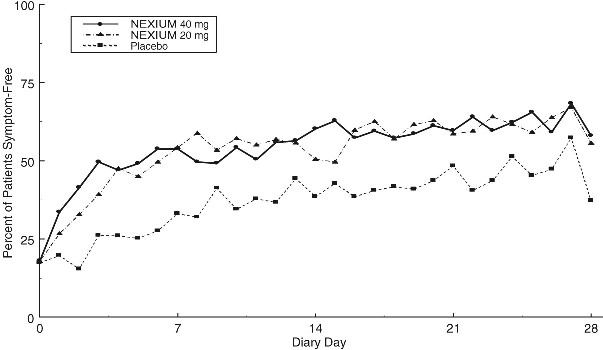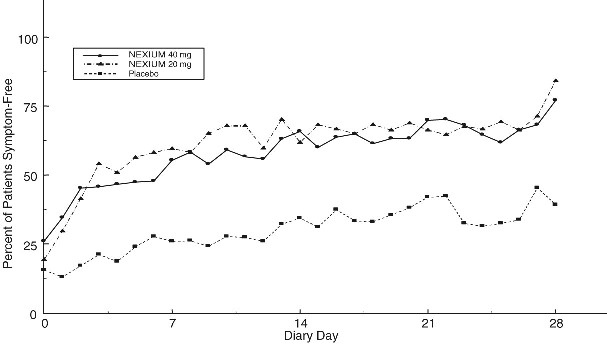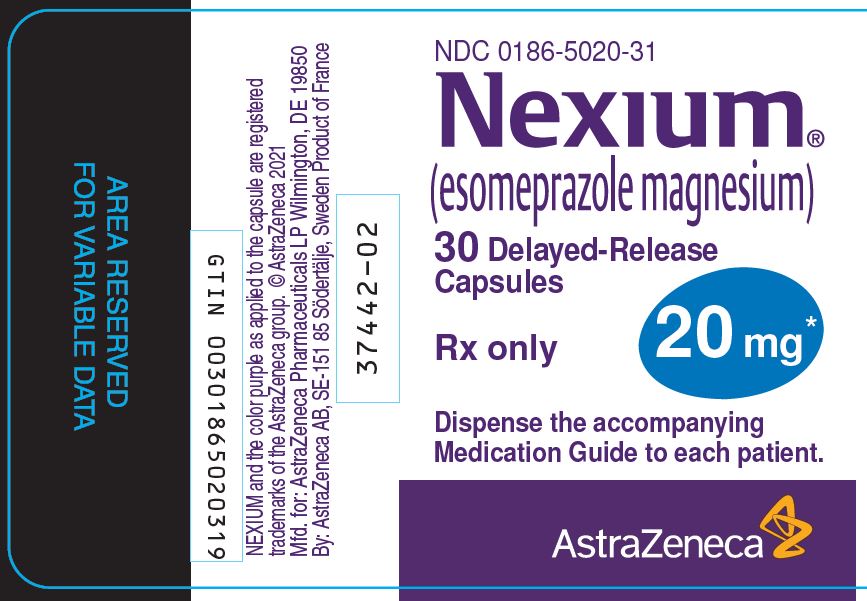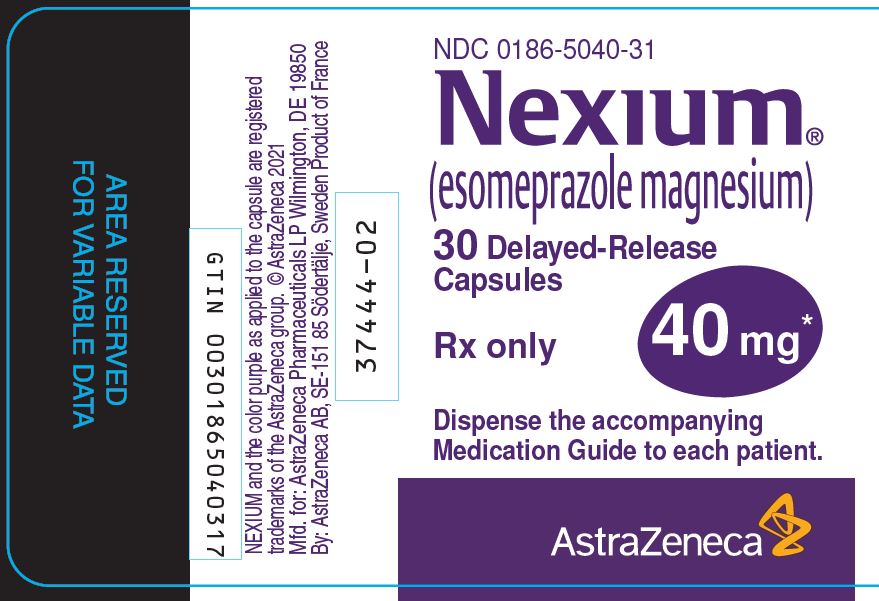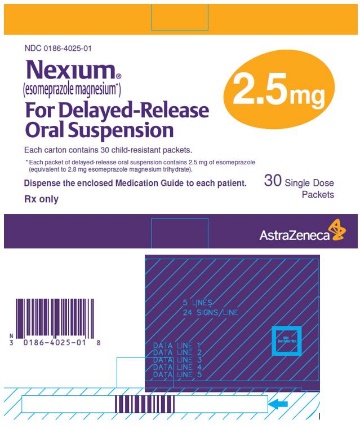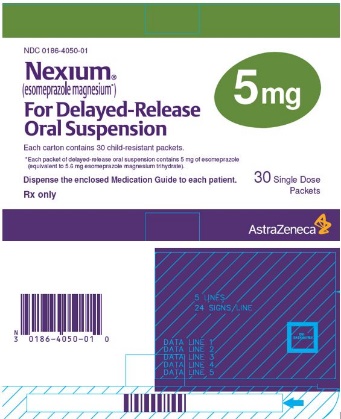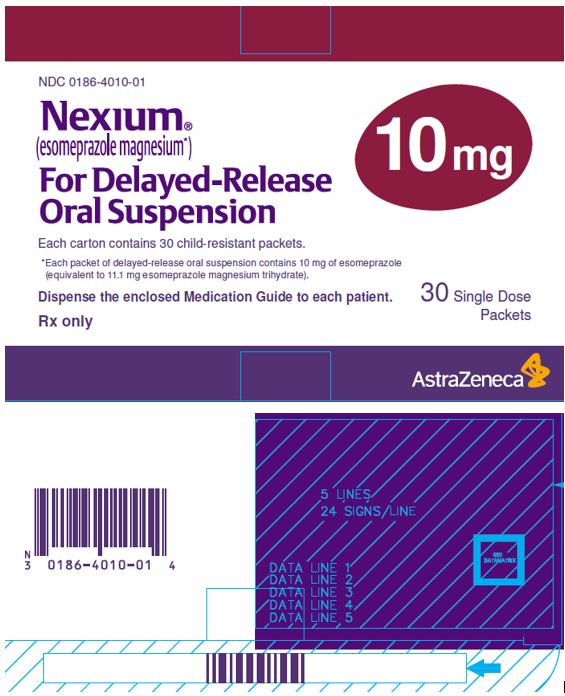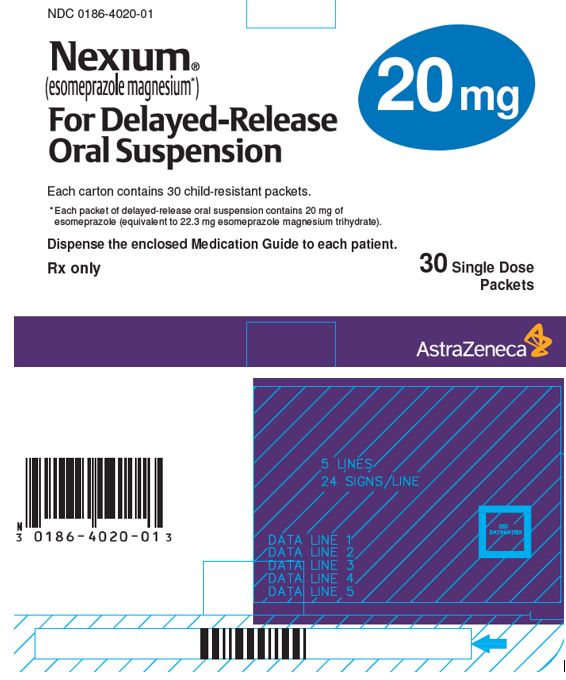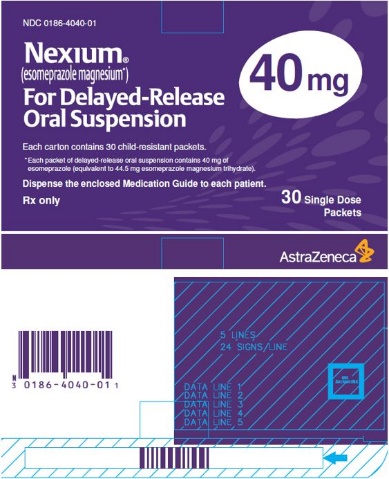 DRUG LABEL: NEXIUM
NDC: 0186-5020 | Form: CAPSULE, DELAYED RELEASE
Manufacturer: AstraZeneca Pharmaceuticals LP
Category: prescription | Type: HUMAN PRESCRIPTION DRUG LABEL
Date: 20251219

ACTIVE INGREDIENTS: ESOMEPRAZOLE MAGNESIUM TRIHYDRATE 20 mg/1 1
INACTIVE INGREDIENTS: GLYCERYL MONOSTEARATE; HYDROXYPROPYL CELLULOSE (1600000 WAMW); HYPROMELLOSE, UNSPECIFIED; MAGNESIUM STEARATE; METHACRYLIC ACID; TALC; TRIETHYL CITRATE; POLYSORBATE 80; GELATIN, UNSPECIFIED; FD&C BLUE NO. 1; FD&C RED NO. 40; D&C RED NO. 28; TITANIUM DIOXIDE; ALCOHOL; ISOPROPYL ALCOHOL; BUTYL ALCOHOL; POLYETHYLENE GLYCOL, UNSPECIFIED; SODIUM HYDROXIDE; POVIDONE, UNSPECIFIED; D&C YELLOW NO. 10

HIGHLIGHTS OF PRESCRIBING INFORMATION

These highlights do not include all the information needed to use NEXIUM safely and effectively. See full prescribing information for NEXIUM.
NEXIUM® (esomeprazole magnesium) delayed-release capsules, for oral use
NEXIUM® (esomeprazole magnesium) for delayed-release oral suspension
Initial U.S. Approval: 1989 (omeprazole)

1 INDICATIONS AND USAGE

NEXIUM is a proton pump inhibitor (PPI).

NEXIUM delayed-release capsules and NEXIUM for delayed-release oral

suspension are indicated for the:

- Short-term treatment in the healing of erosive esophagitis (EE) in adults and pediatric patients 12 years to 17 years of age. (1.1)
- Maintenance of healing of EE in adults. (1.2)
- Short-term treatment of heartburn and other symptoms associated GERD in adults and pediatric patients 12 years to 17 years of age. (1.3)
- Risk reduction of nonsteroidal anti-inflammatory drugs (NSAID)-associated gastric ulcer in adults at risk for developing gastric ulcers due to age (60 years and older) and/or documented history of gastric ulcers. (1.4)
- Helicobacter pylori eradication in adult patients to reduce the risk of duodenal ulcer recurrence in combination with amoxicillin and clarithromycin. (1.5)
- Long-term treatment of pathological hypersecretory conditions, including Zollinger-Ellison syndrome in adults. (1.6)

NEXIUM for delayed-release oral suspension is indicated for the:

- Short-term treatment in the healing of EE in pediatric patients 1 year to 11 years of age and of EE due to acid-mediated GERD in pediatric patients 1 month to less than 1 year of age. (1.1)
- Short-term treatment of heartburn and other symptoms associated with GERD in pediatric patients 1 year to 11 years of age. (1.3)

2 DOSAGE AND ADMINISTRATION

Population | Recommended Adult (2.1) and Pediatric Dosage (2.2)
Healing of EE (1 year and older)
EE due to Acid-Mediated GERD (1 month to less than 1 year)
Adults | 20 mg or 40 mg [A maximum dosage of 20 mg once daily is recommended for patients with severe liver impairment (Child-Pugh Class C).] once daily for 4 to 8 weeks; some patients may require an additional 4 to 8 weeks
12 years to 17 years | 20 mg or 40 mg once daily for 4 to 8 weeks
1 month to 11 years | see full prescribing information for weight-based dosing and duration of treatment (2.2)
Maintenance of Healing of EE
Adults | 20 mg once daily. Controlled studies do not extend beyond 6 months
Treatment of Symptomatic GERD
Adults | 20 mg once daily once daily for 4 weeks some patients may require an additional 4 weeks
12 years to 17 years | 20 mg once daily for 4 weeks
1 year to 11 years | 10 mg once daily for up to 8 weeks
Risk Reduction of NSAID-Associated Gastric Ulcer
Adults | 20 mg or 40 mg once daily for up to 6 months [Controlled studies do not extend beyond 6 months.]
H. pylori Eradication to Reduce the Risk of Duodenal Ulcer Recurrence
Adults | NEXIUM 40 mg once daily for 10 days
Adults | Amoxicillin 1000 mg twice daily for 10 days [Refer to the amoxicillin and clarithromycin prescribing information for dosage adjustments in elderly and renally-impaired patients.]
Adults | Clarithromycin 500 mg twice daily for 10 days
Pathological Hypersecretory Conditions Including Zollinger-Ellison Syndrome
Adults | Starting dosage is 40 mg twice daily [A starting dosage of 20 mg twice daily is recommended for patients with severe liver impairment (Child-Pugh Class C).] (varies with the individual patient) as long as clinically indicated.

Preparation and Administration Information

- Swallow capsules whole; do not crush or chew. For patients who cannot swallow intact capsule, the capsule can be opened, and the contents mixed with applesauce. (2.3)
- Mix packets with water to create an oral suspension. (2.3)
- Opened capsules can be administered through a nasogastric tube and oral suspension can be administered through a nasogastric or gastric tube. (2.3)

3 DOSAGE FORMS AND STRENGTHS

- Delayed-Release Capsules: 20 mg and 40 mg esomeprazole. (3)
- For Delayed-Release Oral Suspension: 2.5 mg, 5 mg, 10 mg, 20 mg, and 40 mg esomeprazole. (3)

4 CONTRAINDICATIONS

- Known hypersensitivity to substituted benzimidazoles or any component of the formulation. (4)
- Patients receiving rilpivirine-containing products. (4, 7)
- Refer to the Contraindications section of the prescribing information for amoxicillin and clarithromycin, when administered in combination with NEXIUM. (4)

5 WARNINGS AND PRECAUTIONS

- Gastric Malignancy: In adults, symptomatic response does not preclude the presence of gastric malignancy. Consider additional follow-up and diagnostic testing. (5.1)
- Acute Tubulointerstitial Nephritis: Discontinue treatment and evaluate patients. (5.2)
- Clostridium difficile-Associated Diarrhea: PPI therapy may be associated with increased risk. (5.3)
- Bone Fracture: Long-term and multiple daily dose PPI therapy may be associated with an increased risk for osteoporosis-related fractures of the hip, wrist or spine. (5.4)
- Severe Cutaneous Adverse Reactions: Discontinue at the first signs or symptoms of severe cutaneous adverse reactions or other signs of hypersensitivity and consider further evaluation. (5.5)
- Cutaneous and Systemic Lupus Erythematosus: Mostly cutaneous; new onset or exacerbation of existing disease; discontinue NEXIUM and refer to specialist for evaluation. (5.6)
- Interaction with Clopidogrel: Avoid concomitant use of NEXIUM. (5.7)
- Cyanocobalamin (Vitamin B-12) Deficiency: Daily long-term use (e.g., longer than 3 years) may lead to malabsorption or a deficiency of cyanocobalamin. (5.8)
- Hypomagnesemia and Mineral Metabolism: Reported rarely with prolonged treatment with PPIs. (5.9)
- Interaction with St. John’s Wort or Rifampin: Avoid concomitant use of NEXIUM. (5.10, 7)
- Interactions with Diagnostic Investigations for Neuroendocrine Tumors: Increased chromogranin A (CgA) levels may interfere with diagnostic investigations for neuroendocrine tumors, temporarily stop NEXIUM at least 14 days before assessing CgA levels. (5.11, 12.2)
- Interaction with Methotrexate: Concomitant use with PPIs may elevate and/or prolong serum concentrations of methotrexate and/or its metabolite, possibly leading to toxicity. With high dose methotrexate administration, consider temporary withdrawal of NEXIUM. (5.12, 7)
- Fundic Gland Polyps: Risk increases with long-term use, especially beyond one year. Use the shortest duration of therapy. (5.13)

6 ADVERSE REACTIONS

Most common adverse reactions (6.1):

- Adults (≥ 18 years) (>1%) are: headache, diarrhea, nausea, flatulence, abdominal pain, constipation, and dry mouth.
- Pediatrics (1 to 17 years) (>2%) are: headache, diarrhea, abdominal pain, nausea, and somnolence.
- Pediatrics (1 month to less than 1 year) (>1%) are: abdominal pain, regurgitation, tachypnea, and increased ALT.

To report SUSPECTED ADVERSE REACTIONS, contact AstraZeneca at 1-800-236-9933 or FDA at 1-800-FDA-1088 or www.fda.gov/medwatch.

7 DRUG INTERACTIONS

See full prescribing information for a list of clinically important drug

interactions. (7)

8 USE IN SPECIFIC POPULATIONS

Pediatrics: Use is not recommended for the treatment of symptomatic GERD in patients 1 month to less than 1 year of age; efficacy was not demonstrated. (8.4)

FULL PRESCRIBING INFORMATION

1 INDICATIONS AND USAGE

1.1 Healing of Erosive Esophagitis (EE)

Adults

NEXIUM delayed-release capsules and NEXIUM for delayed-release oral suspension are indicated for the short-term treatment (4 to 8 weeks) in the healing and symptomatic resolution of diagnostically confirmed EE in adults. For those patients who have not healed after 4 to 8 weeks of treatment, an additional 4- to 8- week course of NEXIUM may be considered.

Pediatric Patients 12 Years to 17 Years of Age

NEXIUM delayed-release capsules and NEXIUM for delayed-release oral suspension are indicated for the short-term treatment (4 to 8 weeks) for the healing of EE in pediatric patients 12 years to 17 years of age.

Pediatric Patients 1 Year to 11 Years of Age

NEXIUM for delayed-release oral suspension is indicated for the short-term treatment (8 weeks) for the healing of EE in pediatric patients 1 year to 11 years of age.

Pediatric Patients 1 Month to Less Than 1 Year of Age

NEXIUM for delayed-release oral suspension is indicated for short-term treatment (up to 6 weeks) of EE due to acid-mediated GERD in pediatric patients 1 month to less than 1 year of age.

1.2 Maintenance of Healing of EE

NEXIUM delayed-release capsules and NEXIUM for delayed-release oral suspension are indicated for the maintenance of healing of EE in adults. Controlled studies do not extend beyond 6 months.

1.3 Treatment of Symptomatic GERD

Adults

NEXIUM delayed-release capsules and NEXIUM for delayed-release oral suspension are indicated for short-term treatment (4 to 8 weeks) of heartburn and other symptoms associated with GERD in adults.

Pediatric Patients 12 Years to 17 Years of Age

NEXIUM delayed-release capsules and NEXIUM for delayed-release oral suspension are indicated for short-term treatment (4 weeks) of heartburn and other symptoms associated with GERD in pediatric patients 12 years to 17 years of age.

Pediatric Patients 1 Year to 11 Years of Age

NEXIUM for delayed-release oral suspension is indicated for short-term treatment (up to 8 weeks) of heartburn and other symptoms associated with GERD in pediatric patients 1 year to 11 years of age.

1.4 Risk Reduction of Nonsteroidal Anti-Inflammatory Drugs (NSAID)-Associated Gastric Ulcer

NEXIUM delayed-release capsules and NEXIUM for delayed-release oral suspension are indicated for the reduction in

the occurrence of gastric ulcers associated with continuous NSAID therapy in adult patients at risk for developing gastric ulcers. Patients are considered to be at risk due to their age (60 years and older) and/or documented history of gastric

ulcers. Controlled studies do not extend beyond 6 months.

1.5 Helicobacter pylori Eradication to Reduce the Risk of Duodenal Ulcer Recurrence

Eradication of H. pylori has been shown to reduce the risk of duodenal ulcer recurrence.

Triple Therapy

NEXIUM delayed-release capsules or NEXIUM for delayed-release oral suspension in combination with amoxicillin and clarithromycin is indicated for the treatment of adult patients with H. pylori infection and duodenal ulcer disease (active or history of within the past 5 years) to eradicate H. pylori.

In patients who fail therapy, susceptibility testing should be done. If resistance to clarithromycin is demonstrated or susceptibility testing is not possible, alternative antimicrobial therapy should be instituted [see Clinical Pharmacology (12.4) and the prescribing information for clarithromycin].

1.6 Pathological Hypersecretory Conditions Including Zollinger-Ellison Syndrome

NEXIUM delayed-release capsules and NEXIUM for delayed-release oral suspension are indicated for the long-term treatment of pathological hypersecretory conditions, including Zollinger-Ellison Syndrome, in adults.

2 DOSAGE AND ADMINISTRATION

2.1 Recommended Dosage in Adults by Indication

Table 1 shows the recommended adult dosage of NEXIUM by indication.

The duration of NEXIUM treatment should be based on available safety and efficacy data specific to the defined indication and dosing frequency and individual patient medical needs. NEXIUM should only be initiated and continued if the benefits outweigh the risks of treatment.

Table 1: Recommended Dosage of NEXIUM in Adults by Indication
Adult Indication | Recommended Dosage of; NEXIUM delayed-release capsules and NEXIUM for delayed-release oral suspension | Treatment Duration
Healing of EE | 20 mg or 40 mg [A maximum dosage of 20 mg once daily is recommended for patients with severe liver impairment (Child-Pugh Class C) [see Use in Specific Populations (8.6)].] once daily | 4 to 8 weeks [Most patients are healed within 4 to 8 weeks. For patients who do not heal after 4 to 8 weeks, an additional 4 to 8 weeks of treatment may be required to achieve healing [see Clinical Studies (14.1)].]
Maintenance of Healing of EE | 20 mg once daily | Controlled studies do not extend beyond 6 months
Treatment of Symptomatic GERD | 20 mg once daily | 4 weeks; if symptoms do not resolve completely, consider an additional 4 weeks
Risk Reduction of NSAID-Associated Gastric Ulcer | 20 mg or 40 mg once daily | Controlled studies do not extend beyond 6 months
H. pylori Eradication to Reduce the Risk of Duodenal Ulcer Recurrence (Triple Therapy) | NEXIUM 40 mg once daily | 10 days
H. pylori Eradication to Reduce the Risk of Duodenal Ulcer Recurrence (Triple Therapy) | Amoxicillin 1000 mg twice daily [Refer to the amoxicillin and clarithromycin prescribing information for dosage adjustments in elderly and renally-impaired patients.] | 10 days
H. pylori Eradication to Reduce the Risk of Duodenal Ulcer Recurrence (Triple Therapy) | Clarithromycin 500 mg twice daily | 10 days
Pathological Hypersecretory Conditions Including Zollinger-Ellison Syndrome | Starting dosage is 40 mg twice daily [A starting dosage of 20 mg twice daily is recommended for patients with severe liver impairment (Child-Pugh Class C) [see Use in Specific Populations (8.6)].] ; individualize the regimen to patient needs.; Dosages of up to 240 mg/day have been administered [see Clinical Studies (14.7)]. | As long as clinically indicated

2.2 Recommended Dosage in Pediatric Patients by Indication

Table 2 shows the recommended dosage of NEXIUM in pediatric patients by indication.

Table 2: Recommended Dosage of NEXIUM in Pediatric Patients by Indication
Indication | Patient Age | Recommended Dosage | Duration
Healing of EE | 12 years to 17 years | NEXIUM delayed-release capsules or NEXIUM for delayed-release oral suspension:; 20 mg or 40 mg once daily | 4 to 8 Weeks
Healing of EE | 1 year to 11 years [Dosages over 1 mg/kg/day have not been studied] | NEXIUM for delayed-release oral suspension:; Less than 20 kg; 10 mg once daily; 20 kg and greater; 10 mg or 20 mg once daily | 8 weeks
Treatment of EE due to Acid-Mediated GERD | 1 month to less than 1 year [Dosages over 1.33 mg/kg/day have not been studied] | NEXIUM for delayed-release oral suspension:; 3 kg to 5 kg; 2.5 mg once daily; Greater than 5 kg to 7.5 kg; 5 mg once daily; Greater than 7.5 kg to 12 kg; 10 mg once daily | Up to 6 weeks
Treatment of Symptomatic GERD | 12 years to 17 years | NEXIUM delayed-release capsules or NEXIUM for delayed-release oral suspension:; 20 mg once daily | 4 weeks
Treatment of Symptomatic GERD | 1 year to 11 years | NEXIUM for delayed-release oral suspension:; 10 mg once daily^1 | Up to 8 weeks

2.3 Preparation and Administration Instructions

- Take NEXIUM delayed-release capsules and NEXIUM for delayed-release oral suspension at least one hour before meals [see Clinical Pharmacology (12.3)].
- Antacids may be used concomitantly with NEXIUM.
- Take a missed dose as soon as possible. If it is almost time for the next dose, skip the missed dose and take the next dose at the regular scheduled time. Do not take 2 doses at the same time.

NEXIUM Delayed-Release Capsules

Administer NEXIUM delayed-release capsules orally or via a nasogastric tube, as described below.

Oral Administration

- Swallow NEXIUM delayed-release capsules whole; do not chew or crush the capsules.
- For patients who have difficulty swallowing capsules, NEXIUM delayed-release capsules can be opened, and the contents sprinkled on applesauce. Use with other foods has not been evaluated and is not recommended.
1. Add one tablespoon of applesauce to an empty bowl. The applesauce used should not be hot and should be soft enough to be swallowed without chewing.
2. Open the NEXIUM delayed-release capsule and carefully empty the granules inside the capsule onto the applesauce.
3. Mix the granules with the applesauce.
4. Administer the mixture immediately. Do not chew or crush the granules
5. Discard any remaining mixture. Do not store the mixture for future use.

Administration via Nasogastric Tube

1. Open the NEXIUM delayed-release capsule and empty the granules into a 60 mL catheter-tipped syringe.
2. Mix the granules with 50 mL of water.
3. Replace the plunger and shake the catheter-tipped syringe vigorously for 15 seconds.
4. Hold the catheter-tipped syringe with the tip up and check for any granules remaining in the tip.
5. Attach the catheter-tipped syringe to a nasogastric tube and deliver the contents of the syringe through the nasogastric tube into the stomach.
6. After administering the granules, flush the nasogastric tube with additional water.
7. Use the mixture immediately after preparation. Do not administer the granules if they have dissolved or disintegrated.

NEXIUM For Delayed-Release Oral Suspension

Administer NEXIUM for delayed-release oral suspension orally or via a nasogastric or gastric tube, as described below.

Oral Administration

1. Empty the contents of a 2.5 mg or 5 mg NEXIUM packet into a container containing 5 mL of water. For the 10 mg, 20 mg, and 40 mg strengths, the contents of a packet should be emptied into a container containing 15 mL of water. If two packets are needed, mix in a similar way add twice the required amount of water.
2. Stir the packet contents into the water.
3. Leave 2 to 3 minutes to thicken.
4. Stir and drink within 30 minutes.
5. If any of the contents remain after drinking, add more water, stir, and drink immediately.

Administration via Nasogastric or Gastric Tube

1. Add 5 mL of water to a catheter-tipped syringe and then add the contents of a 2.5 mg or 5 mg NEXIUM packet. For the 10 mg, 20 mg, and 40 mg packet strengths, add at least 15 mL of water to the catheter-tipped syringe.
2. Immediately shake the catheter-tipped syringe and leave 2 to 3 minutes to thicken.
3. Shake the catheter-tipped syringe and inject through the nasogastric or gastric tube, French size 6 or larger, into the stomach within 30 minutes.
4. Refill the catheter-tipped syringe with an equal amount of water (5 mL or 15 mL).
5. Shake and flush any remaining contents from the nasogastric or gastric tube into the stomach.

3 DOSAGE FORMS AND STRENGTHS

NEXIUM Delayed-Release Capsules

- 20 mg esomeprazole in opaque, hard gelatin, amethyst colored capsules with two radial bars in yellow on the cap and NEXIUM 20 mg in yellow on the body.
- 40 mg esomeprazole in opaque, hard gelatin, amethyst colored capsules with three radial bars in yellow on the cap and NEXIUM 40 mg in yellow on the body.

NEXIUM For Delayed-Release Oral Suspension

- 2.5 mg, 5 mg, 10 mg, 20 mg or 40 mg esomeprazole in unit dose packets containing a fine yellow powder, consisting of white to pale brownish esomeprazole granules and pale-yellow inactive granules.

4 CONTRAINDICATIONS

- NEXIUM is contraindicated in patients with known hypersensitivity to substituted benzimidazoles or to any component of the formulation. Hypersensitivity reactions may include anaphylaxis, anaphylactic shock, angioedema, bronchospasm, acute tubulointerstitial nephritis, and urticaria [see Warnings and Precautions (5.2), Adverse Reactions (6.2)].
- For information about contraindications of amoxicillin and clarithromycin, indicated in combination with NEXIUM for H. pylori eradication to reduce the risk of duodenal ulcer recurrence, refer to the Contraindications section of the respective prescribing information.
- Proton pump inhibitors (PPIs), including NEXIUM, are contraindicated in patients receiving rilpivirine-containing products [see Drug Interactions (7)].

5 WARNINGS AND PRECAUTIONS

5.1 Presence of Gastric Malignancy

In adults, symptomatic response to therapy with NEXIUM does not preclude the presence of gastric malignancy. Consider additional follow-up and diagnostic testing in adult patients who have a suboptimal response or an early symptomatic relapse after completing treatment with a PPI. In older patients, also consider an endoscopy.

5.2 Acute Tubulointerstitial Nephritis

Acute tubulointerstitial nephritis (TIN) has been observed in patients taking PPIs and may occur at any point during PPI therapy. Patients may present with varying signs and symptoms from symptomatic hypersensitivity reactions to non-specific symptoms of decreased renal function (e.g., malaise, nausea, anorexia). In reported case series, some patients were diagnosed on biopsy and in the absence of extra-renal manifestations (e.g., fever, rash or arthralgia). Discontinue NEXIUM and evaluate patients with suspected acute TIN [see Contraindications (4)].

5.3 Clostridium difficile-Associated Diarrhea

Published observational studies suggest that PPI therapy like NEXIUM may be associated with an increased risk of Clostridium difficile-associated diarrhea, especially in hospitalized patients. This diagnosis should be considered for diarrhea that does not improve [see Adverse Reactions (6.2)].

Patients should use the lowest dose and shortest duration of PPI therapy appropriate to the condition being treated.

Clostridium difficile-associated diarrhea (CDAD) has been reported with use of nearly all antibacterial agents. For more information specific to antibacterial agents (clarithromycin and amoxicillin) indicated for use in combination with NEXIUM, refer to Warnings and Precautions section of the corresponding prescribing information.

5.4 Bone Fracture

Several published observational studies suggest that proton pump inhibitor (PPI) therapy may be associated with an increased risk for osteoporosis-related fractures of the hip, wrist, or spine. The risk of fracture was increased in patients who received high-dose, defined as multiple daily doses, and long-term PPI therapy (a year or longer). Patients should use the lowest dose and shortest duration of PPI therapy appropriate to the condition being treated. Patients at risk for osteoporosis-related fractures should be managed according to established treatment guidelines [see Dosage and Administration (2) and Adverse Reactions (6.2)].

5.5 Severe Cutaneous Adverse Reactions

Severe cutaneous adverse reactions, including Stevens-Johnson syndrome (SJS) and toxic epidermal necrolysis (TEN), drug reaction with eosinophilia and systemic symptoms (DRESS), and acute generalized exanthematous pustulosis (AGEP) have been reported in association with the use of PPIs [see Adverse Reactions (6.2)]. Discontinue NEXIUM at the first signs or symptoms of severe cutaneous adverse reactions or other signs of hypersensitivity and consider further evaluation.

5.6 Cutaneous and Systemic Lupus Erythematosus

Cutaneous lupus erythematosus (CLE) and systemic lupus erythematosus (SLE) have been reported in patients taking PPIs, including esomeprazole. These events have occurred as both new onset and an exacerbation of existing autoimmune disease. The majority of PPI-induced lupus erythematosus cases were CLE.

The most common form of CLE reported in patients treated with PPIs was subacute CLE (SCLE) and occurred within weeks to years after continuous drug therapy in patients ranging from infants to the elderly. Generally, histological findings were observed without organ involvement.

Systemic lupus erythematosus (SLE) is less commonly reported than CLE in patients receiving PPIs. PPI associated SLE is usually milder than non-drug induced SLE. Onset of SLE typically occurred within days to years after initiating treatment primarily in patients ranging from young adults to the elderly. The majority of patients presented with rash; however, arthralgia and cytopenia were also reported.

Avoid administration of PPIs for longer than medically indicated. If signs or symptoms consistent with CLE or SLE are noted in patients receiving NEXIUM, discontinue the drug and refer the patient to the appropriate specialist for evaluation. Most patients improve with discontinuation of the PPI alone in 4 to 12 weeks. Serological testing (e.g., ANA) may be positive and elevated serological test results may take longer to resolve than clinical manifestations.

5.7 Interaction with Clopidogrel

Avoid concomitant use of NEXIUM with clopidogrel. Clopidogrel is a prodrug. Inhibition of platelet aggregation by clopidogrel is entirely due to an active metabolite. The metabolism of clopidogrel to its active metabolite can be impaired by use with concomitant medications, such as esomeprazole, that inhibit CYP2C19 activity. Concomitant use of clopidogrel with 40 mg esomeprazole reduces the pharmacological activity of clopidogrel. When using NEXIUM consider alternative anti-platelet therapy [see Drug Interactions (7)].

5.8 Cyanocobalamin (Vitamin B-12) Deficiency

Daily treatment with any acid-suppressing medications over a long period of time (e.g., longer than 3 years) may lead to malabsorption of cyanocobalamin (vitamin B-12) caused by hypo- or achlorhydria. Rare reports of cyanocobalamin deficiency occurring with acid-suppressing therapy have been reported in the literature. This diagnosis should be considered if clinical symptoms consistent with cyanocobalamin deficiency are observed.

5.9 Hypomagnesemia and Mineral Metabolism

Hypomagnesemia, symptomatic and asymptomatic, has been reported rarely in patients treated with PPIs for at least three months, in most cases after a year of therapy. Serious adverse events include tetany, arrhythmias, and seizures. Hypomagnesemia may lead to hypocalcemia and/or hypokalemia and may exacerbate underlying hypocalcemia in at-risk

patients. In most patients, treatment of hypomagnesemia required magnesium replacement and discontinuation of the PPI.

For patients expected to be on prolonged treatment or who take PPIs with medications such as digoxin or drugs that may cause hypomagnesemia (e.g., diuretics), health care professionals may consider monitoring magnesium levels prior to initiation of PPI treatment and periodically [see Adverse Reactions (6.2)].

Consider monitoring magnesium and calcium levels prior to initiation of NEXIUM and periodically while on treatment in patients with a preexisting risk of hypocalcemia (e.g., hypoparathyroidism). Supplement with magnesium and/or calcium, as necessary. If hypocalcemia is refractory to treatment, consider discontinuing the PPI.

5.10 Interaction with St. John’s Wort or Rifampin

Drugs which induce CYP2C19 or CYP3A4 (such as St. John’s Wort or rifampin) can substantially decrease esomeprazole concentrations [see Drug Interactions (7)]. Avoid concomitant use of NEXIUM with St. John’s Wort or rifampin.

5.11 Interactions with Diagnostic Investigations for Neuroendocrine Tumors

Serum chromogranin A (CgA) levels increase secondary to drug-induced decreases in gastric acidity. The increased CgA level may cause false positive results in diagnostic investigations for neuroendocrine tumors. Healthcare providers should temporarily stop esomeprazole treatment at least 14 days before assessing CgA levels and consider repeating the test if initial CgA levels are high. If serial tests are performed (e.g., for monitoring), the same commercial laboratory should be used for testing, as reference ranges between tests may vary [see Clinical Pharmacology (12.2)].

5.12 Interaction with Methotrexate

Literature suggests that concomitant use of PPIs with methotrexate (primarily at high dose; see methotrexate prescribing information) may elevate and prolong serum levels of methotrexate and/or its metabolite, possibly leading to methotrexate toxicities. In high-dose methotrexate administration a temporary withdrawal of the PPI may be considered in some patients [see Drug Interactions (7)].

5.13 Fundic Gland Polyps

PPI use is associated with an increased risk of fundic gland polyps that increases with long-term use, especially beyond one year. Most PPI users who developed fundic gland polyps were asymptomatic and fundic gland polyps were identified incidentally on endoscopy. Use the shortest duration of PPI therapy appropriate to the condition being treated.

6 ADVERSE REACTIONS

The following serious adverse reactions are described below and elsewhere in labeling:

- Acute Tubulointerstitial Nephritis [see Warnings and Precautions (5.2)]
- Clostridium difficile-Associated Diarrhea [see Warnings and Precautions (5.3)]
- Bone Fracture [see Warnings and Precautions (5.4)]
- Severe Cutaneous Adverse Reactions [see Warnings and Precautions (5.5)]
- Cutaneous and Systemic Lupus Erythematosus [see Warnings and Precautions (5.6)]
- Cyanocobalamin (Vitamin B-12) Deficiency [see Warnings and Precautions (5.8)]
- Hypomagnesemia and Mineral Metabolism [see Warnings and Precautions (5.9)]
- Fundic Gland Polyps [see Warnings and Precautions (5.13)]

6.1 Clinical Trials Experience

Because clinical trials are conducted under widely varying conditions, adverse reaction rates observed in the clinical trials of a drug cannot be directly compared to rates in the clinical trials of another drug and may not reflect the rates observed in practice.

Adults

The safety of NEXIUM delayed-release capsules was evaluated in over 15,000 patients (aged 18 to 84 years) in clinical trials worldwide including over 8,500 patients in the United States and over 6,500 patients in Europe and Canada. Over 2,900 patients were treated in long-term studies for up to 6 to 12 months.

The safety in the treatment of healing of EE in adults was assessed in four randomized comparative clinical trials, which included 1,240 patients who received NEXIUM 20 mg once daily, 2,434 patients on NEXIUM 40 mg once daily, and 3,008 patients on omeprazole 20 mg once daily. The most frequently occurring adverse reactions (at least 1%) in all three groups were headache (5.5%, 5%, and 3.8%, respectively) and diarrhea (no difference among the three groups). Nausea, flatulence, abdominal pain, constipation, and dry mouth occurred at similar rates among patients taking NEXIUM or omeprazole.

Less common adverse reactions with an incidence of less than 1% are listed below by body system:

Body as a Whole: abdomen enlarged, allergic reaction, asthenia, back pain, chest pain, substernal chest pain, facial edema, peripheral edema, hot flushes, fatigue, fever, flu-like disorder, generalized edema, leg edema, malaise, pain, rigors;

Cardiovascular: flushing, hypertension, tachycardia;

Endocrine: goiter;

Gastrointestinal: bowel irregularity, constipation aggravated, dyspepsia, dysphagia, dysplasia GI, epigastric pain, eructation, esophageal disorder, frequent stools, gastroenteritis, GI hemorrhage, GI symptoms not otherwise specified, hiccup, melena, mouth disorder, pharynx disorder, rectal disorder, serum gastrin increased, tongue disorder, tongue edema, ulcerative stomatitis, vomiting;

Hearing: earache, tinnitus;

Hematologic: anemia, anemia hypochromic, cervical lymphadenopathy, epistaxis, leukocytosis, leukopenia, thrombocytopenia;

Hepatic: bilirubinemia, hepatic function abnormal, SGOT increased, SGPT increased;

Metabolic/Nutritional: glycosuria, hyperuricemia, hyponatremia, increased alkaline phosphatase, thirst, vitamin B12 deficiency, weight increase, weight decrease;

Musculoskeletal: arthralgia, arthritis aggravated, arthropathy, cramps, fibromyalgia syndrome, hernia, polymyalgia rheumatica;

Nervous System/Psychiatric: anorexia, apathy, appetite increased, confusion, depression aggravated, dizziness, hypertonia, nervousness, hypoesthesia, impotence, insomnia, migraine, migraine aggravated, paresthesia, sleep disorder, somnolence, tremor, vertigo, visual field defect;

Reproductive: dysmenorrhea, menstrual disorder, vaginitis;

Respiratory: asthma aggravated, coughing, dyspnea, larynx edema, pharyngitis, rhinitis, sinusitis;

Skin and Appendages: acne, angioedema, dermatitis, pruritus, pruritus ani, rash, rash erythematous, rash maculo-papular, skin inflammation, sweating increased, urticaria;

Special Senses: otitis media, parosmia, taste loss, taste perversion;

Urogenital: abnormal urine, albuminuria, cystitis, dysuria, fungal infection, hematuria, micturition frequency, moniliasis, genital moniliasis, polyuria;

Visual: conjunctivitis, vision abnormal.

The following potentially clinically significant laboratory changes in clinical trials, irrespective of relationship to NEXIUM, were reported in 1% or less of patients: increased creatinine, uric acid, total bilirubin, alkaline phosphatase, ALT, AST, hemoglobin, white blood cell count, platelets, serum gastrin, potassium, sodium, thyroxine and thyroid stimulating hormone [see Clinical Pharmacology (12.2)]. Decreases were seen in hemoglobin, white blood cell count, platelets, potassium, sodium, and thyroxine.

Endoscopic findings that were reported as adverse reactions include: duodenitis, esophagitis, esophageal stricture, esophageal ulceration, esophageal varices, gastric ulcer, gastritis, hernia, benign polyps or nodules, Barrett’s esophagus, and mucosal discoloration.

The incidence of adverse reactions during 6-month trials for the maintenance of healing of EE with NEXIUM 20 mg once daily was similar to placebo. There were no differences in types of adverse reactions seen during maintenance treatment up to 12 months compared to short-term treatment.

Two placebo-controlled studies were conducted in 710 adult patients for the treatment of symptomatic GERD. The most common adverse reactions that were reported were: diarrhea (4%), headache (4%), and abdominal pain (4%).

Combination Treatment with NEXIUM, Amoxicillin and Clarithromycin

In clinical trials of H. pylori eradication of to reduce duodenal ulcer recurrence, no additional adverse reactions specific to the combination of NEXIUM delayed-release capsules, amoxicillin and clarithromycin were observed and were similar to those observed with NEXIUM, amoxicillin, or clarithromycin alone. The most frequently reported adverse reactions for patients who received NEXIUM, amoxicillin and clarithromycin for 10 days were diarrhea (9%), taste perversion (4%), and abdominal pain (4%). No adverse reactions were observed at higher rates with NEXIUM, amoxicillin and clarithromycin than were observed with NEXIUM alone.

In clinical trials using of NEXIUM, amoxicillin and clarithromycin, no additional increased laboratory abnormalities particular to these drug combinations were observed.

For more information on adverse reactions and laboratory changes with amoxicillin or clarithromycin, refer to Adverse Reactions section of the respective prescribing information.

Pediatrics

1 Year to 17 Years of Age

The safety of NEXIUM delayed-release capsules and NEXIUM for delayed-release oral suspension was evaluated in 316 pediatric and adolescent patients aged 1 year to 17 years in four clinical trials for the treatment of symptomatic GERD [see Clinical Studies (14.3)]. In 109 pediatric patients aged 1 year to 11 years, the most frequently reported (at least 1%) treatment-related adverse reactions in these patients were diarrhea (3%), headache (2%) and somnolence (2%). In 149 pediatric patients aged 12 years to 17 years the most frequently reported adverse reactions (at least 2%) were headache (8%), abdominal pain (3%), diarrhea (2%), and nausea (2%).

1 Month to Less Than 1 Year of Age

The safety of esomeprazole magnesium was evaluated in 167 infants from 1 month to less than 1 year of age with GERD in three clinical trials [see Use in Specific Populations (8.4)]. In a study that included 43 pediatric patients, the most frequently reported adverse reactions (at least 5%) with esomeprazole magnesium were irritability and vomiting. In a study that included 98 pediatric patients, administered esomeprazole magnesium for up to 6 weeks (including 39 patients randomized to the withdrawal phase), reported adverse reactions were: abdominal pain (1%), regurgitation (1%),

tachypnea (1%), and increased ALT (1%).

6.2 Postmarketing Experience

The following adverse reactions have been identified during post-approval use of esomeprazole. Because these reactions are reported voluntarily from a population of uncertain size, it is not always possible to reliably estimate their frequency or establish a causal relationship to drug exposure. These reports are listed below by body system:

Blood and Lymphatic: agranulocytosis, pancytopenia;

Eye: blurred vision;

Gastrointestinal: pancreatitis; stomatitis; microscopic colitis; fundic gland polyps;

Hepatobiliary: hepatic failure, hepatitis with or without jaundice;

Immune System: anaphylactic reaction/shock; systemic lupus erythematosus;

Infections and Infestations: GI candidiasis; Clostridium difficile-associated diarrhea;

Metabolism and nutritional disorders: hypomagnesemia (may lead to hypocalcemia and/or hypokalemia) [see Warnings and Precautions (5.9)];

Musculoskeletal and Connective Tissue: muscular weakness, myalgia, bone fracture;

Nervous System: hepatic encephalopathy, taste disturbance;

Psychiatric: aggression, agitation, depression, hallucination;

Renal and Urinary: interstitial nephritis;

Reproductive System and Breast: gynecomastia, erectile dysfunction;

Respiratory, Thoracic, and Mediastinal: bronchospasm;

Skin and Subcutaneous Tissue: alopecia, erythema multiforme, hyperhidrosis, photosensitivity, Stevens-Johnson syndrome, toxic epidermal necrolysis (some fatal), drug reaction with eosinophilia and systemic symptoms (DRESS), and acute generalized exanthematous pustulosis (AGEP), cutaneous lupus erythematosus.

Adverse reactions associated with omeprazole may also be expected to occur with esomeprazole. See the full prescribing information for omeprazole for complete safety information.

7 DRUG INTERACTIONS

Tables 3 and 4 include drugs with clinically important drug interactions and interaction with diagnostics when administered concomitantly with esomeprazole and instructions for preventing or managing them.

Consult the labeling of concomitantly used drugs to obtain further information about interactions with PPIs.

Table 3: Clinically Relevant Interactions Affecting Drugs Co-Administered with Esomeprazole and Interaction with Diagnostics
Antiretrovirals
Clinical Impact: | The effect of PPIs on antiretroviral drugs is variable. The clinical importance and the mechanisms behind these interactions are not always known.; - Decreased exposure of some antiretroviral drugs (e.g., rilpivirine atazanavir, and nelfinavir) when used concomitantly with esomeprazole may reduce antiviral effect and promote the development of drug resistance [see Clinical Pharmacology (12.3)]. - Increased exposure of other antiretroviral drugs (e.g., saquinavir) when used concomitantly with esomeprazole may increase toxicity [see Clinical Pharmacology (12.3)]. - There are other antiretroviral drugs which do not result in clinically relevant interactions with esomeprazole.
Intervention: | Rilpivirine-containing products: Concomitant use with NEXIUM is contraindicated [see Contraindications (4)].; Atazanavir: See prescribing information for atazanavir for dosing information.; Nelfinavir: Avoid concomitant use with NEXIUM. See prescribing information for nelfinavir.; Saquinavir: See the prescribing information for saquinavir for monitoring of potential saquinavir-related toxicities.; Other antiretrovirals: See prescribing information for specific antiretroviral drugs
Warfarin
Clinical Impact: | Increased INR and prothrombin time in patients receiving PPIs, including esomeprazole, and warfarin concomitantly. Increases in INR and prothrombin time may lead to abnormal bleeding and even death.
Intervention: | Monitor INR and prothrombin time and adjust the dose of warfarin, if needed, to maintain the target INR range.
Methotrexate
Clinical Impact: | Concomitant use of esomeprazole with methotrexate (primarily at high dose) may elevate and prolong serum concentrations of methotrexate and/or its metabolite hydroxymethotrexate, possibly leading to methotrexate toxicities. No formal drug interaction studies of high-dose methotrexate with PPIs have been conducted [see Warnings and Precautions (5.12)].
Intervention: | A temporary withdrawal of NEXIUM may be considered in some patients receiving high-dose methotrexate.
2C19 Substrates (e.g., clopidogrel, citalopram, cilostazol)
Clopidogrel
Clinical Impact: | Concomitant use of esomeprazole 40 mg resulted in reduced plasma concentrations of the active metabolite of clopidogrel and a reduction in platelet inhibition [see Clinical Pharmacology (12.3)].; There are no adequate combination studies of a lower dose of esomeprazole or a higher dose of clopidogrel in comparison with the approved dose of clopidogrel.
Intervention: | Avoid concomitant use with NEXIUM Consider use of alternative anti-platelet therapy [see Warnings and Precautions (5.7)].
Citalopram
Clinical Impact: | Increased exposure of citalopram leading to an increased risk of QT prolongation [see Clinical Pharmacology (12.3)].
Intervention: | Limit the dose of citalopram to a maximum of 20 mg per day. See prescribing information for citalopram.
Cilostazol
Clinical Impact: | Increased exposure of cilostazol and one of its active metabolites (3,4-dihydro-cilostazol) [see Clinical Pharmacology (12.3)].
Intervention: | Consider reducing the dose of cilostazol to 50 mg twice daily. See prescribing information for cilostazol.
Digoxin
Clinical Impact: | Potential for increased exposure of digoxin [see Clinical Pharmacology (12.3)].
Intervention: | Monitor digoxin concentrations and adjust the dose, if needed, to maintain therapeutic drug concentrations. See prescribing information for digoxin.
Combination Therapy with Clarithromycin and Amoxicillin
Clinical Impact: | Concomitant administration of clarithromycin with other drugs can lead to serious adverse reactions, including potentially fatal arrhythmias, and are contraindicated.; Amoxicillin also has drug interactions.
Intervention: | See Contraindications, Warnings and Precautions in prescribing information for clarithromycin.; See Drug Interactions in prescribing information for amoxicillin.
Drugs Dependent on Gastric pH for Absorption (e.g., iron salts, erlotinib, dasatinib, nilotinib, mycophenolate mofetil, ketoconazole/itraconazole)
Clinical Impact: | Esomeprazole can reduce the absorption of other drugs due to its effect on reducing intragastric acidity
Intervention: | Mycophenolate mofetil (MMF): Co-administration of omeprazole, of which esomeprazole is an enantiomer, in healthy subjects and in transplant patients receiving MMF has been reported to reduce the exposure to the active metabolite, mycophenolic acid (MPA), possibly due to a decrease in MMF solubility at an increased gastric pH. The clinical relevance of reduced MPA exposure on organ rejection has not been established in transplant patients receiving NEXIUM and MMF. Use NEXIUM with caution in transplant patients receiving MMF [see Clinical Pharmacology (12.3)].; See the prescribing information for other drugs dependent on gastric pH for absorption.
Tacrolimus
Clinical Impact: | Potentially increased exposure of tacrolimus, especially in transplant patients who are intermediate or poor metabolizers of CYP2C19.
Intervention: | Monitor tacrolimus whole blood concentrations and consider reducing the dose, if needed, to maintain therapeutic drug concentrations. See prescribing information for tacrolimus.
Interactions with Investigations of Neuroendocrine Tumors
Clinical Impact: | Serum chromogranin A (CgA) levels increase secondary to PPI-induced decreases in gastric acidity. The increased CgA level may cause false positive results in diagnostic investigations for neuroendocrine tumors [see Warnings and Precautions (5.11), Clinical Pharmacology (12.2)].
Intervention: | Discontinue NEXIUM at least 14 days before assessing CgA levels and consider repeating the test if initial CgA levels are high. If serial tests are performed (e.g. for monitoring), the same commercial laboratory should be used for testing, as reference ranges between tests may vary.
Interaction with Secretin Stimulation Test
Clinical Impact: | Hyper-response in gastrin secretion in response to secretin stimulation test, falsely suggesting gastrinoma.
Intervention: | Discontinue NEXIUM 4 weeks prior to testing [see Clinical Pharmacology (12.2)]
False Positive Urine Tests for THC
Clinical Impact: | There have been reports of false positive urine screening test for tetrahydrocannabinol (THC) in patients receiving PPIs.
Intervention: | An alternative confirmatory method should be considered to verify positive results.

Table 4: Clinically Relevant Interactions Affecting Esomeprazole When Co-Administered with Other Drugs
CYP2C19 or CYP3A4 Inducers
Clinical Impact: | Decreased exposure of esomeprazole when used concomitantly with strong inducers [see Clinical Pharmacology (12.3)].
Intervention: | St. John’s Wort, rifampin: Avoid concomitant use with [see Warnings and Precautions (5.10)].; Ritonavir-containing products: see prescribing information for specific drugs
Voriconazole
Clinical Impact: | Increased exposure of esomeprazole [see Clinical Pharmacology (12.3)].
Intervention: | Dose adjustment of NEXIUM is not normally required. However, in patients with Zollinger-Ellison syndrome, who may require higher doses, dosage adjustment may be considered.; See prescribing information for voriconazole.

8 USE IN SPECIFIC POPULATIONS

8.1 Pregnancy

Risk Summary

There are no adequate and well-controlled studies with esomeprazole in pregnant women. Esomeprazole is the S-isomer of omeprazole. Available epidemiologic data fail to demonstrate an increased risk of major congenital malformations or other adverse pregnancy outcomes with first trimester omeprazole use (see Data). Reproduction studies in rats and rabbits resulted in dose-dependent embryo-lethality at omeprazole doses that were approximately 3.4 to 34 times an oral human dose of 40 mg (based on a body surface area for a 60 kg person).

Teratogenicity was not observed in animal reproduction studies with administration of oral esomeprazole magnesium in rats and rabbits with doses about 68 times and 42 times, respectively, an oral human dose of 40 mg (based on a body surface area basis for a 60 kg person). Changes in bone morphology were observed in offspring of rats dosed through most of pregnancy and lactation at doses equal to or greater than approximately 34 times an oral human dose of 40 mg. When maternal administration was confined to gestation only, there were no effects on bone physeal morphology in the offspring at any age (see Data).

The estimated background risks of major birth defects and miscarriage for the indicated population are unknown. All pregnancies have a background risk of birth defect, loss or other adverse outcomes. In the U.S. general population, the estimated background risk of major birth defects and miscarriage in clinically recognized pregnancies is 2% to 4% and 15% to 20%, respectively.

Data

Human Data

Esomeprazole is the S-isomer of omeprazole. Four epidemiological studies compared the frequency of congenital abnormalities among infants born to women who used omeprazole during pregnancy with the frequency of abnormalities among infants of women exposed to H2-receptor antagonists or other controls.

A population-based retrospective cohort epidemiological study from the Swedish Medical Birth Registry, covering approximately 99% of pregnancies, from 1995 to 1999, reported on 955 infants (824 exposed during the first trimester with 39 of these exposed beyond first trimester, and 131 exposed after the first trimester) whose mothers used omeprazole during pregnancy. The number of infants exposed in utero to omeprazole that had any malformation, low birth weight, low Apgar score, or hospitalization was similar to the number observed in this population. The number of infants born with ventricular septal defects and the number of stillborn infants was slightly higher in the omeprazole-exposed infants than the expected number in this population.

A population-based retrospective cohort study covering all live births in Denmark from 1996 to 2009, reported on 1,800 live births whose mothers used omeprazole during the first trimester of pregnancy and 837,317 live births whose mothers did not use any proton pump inhibitor. The overall rate of birth defects in infants born to mothers with first trimester exposure to omeprazole was 2.9% and 2.6% in infants born to mothers not exposed to any proton pump inhibitor during the first trimester.

A retrospective cohort study reported on 689 pregnant women exposed to either H2-blockers or omeprazole in the first trimester (134 exposed to omeprazole) and 1,572 pregnant women unexposed to either during the first trimester. The overall malformation rate in offspring born to mothers with first trimester exposure to omeprazole, an H2-blocker, or were unexposed was 3.6%, 5.5%, and 4.1% respectively.

A small prospective observational cohort study followed 113 women exposed to omeprazole during pregnancy (89% with first trimester exposures). The reported rate of major congenital malformations was 4% in the omeprazole group, 2% in controls exposed to non-teratogens, and 2.8% in disease paired controls. Rates of spontaneous and elective abortions, preterm deliveries, gestational age at delivery, and mean birth weight were similar among the groups.

Several studies have reported no apparent adverse short-term effects on the infant when single dose oral or intravenous omeprazole was administered to over 200 pregnant women as premedication for cesarean section under general anesthesia.

Animal Data

Omeprazole

Reproductive studies conducted with omeprazole in rats at oral doses up to 138 mg/kg/day (about 34 times an oral human dose of 40 mg on a body surface area basis) and in rabbits at doses up to 69.1 mg/kg/day (about 34 times an oral human dose of 40 mg on a body surface area basis) during organogenesis did not disclose any evidence for a teratogenic potential of omeprazole. In rabbits, omeprazole in a dose range of 6.9 to 69.1 mg/kg/day (about 3.4 to 34 times an oral human dose of 40 mg on a body surface area basis) administered during organogenesis produced dose-related increases in embryo-lethality, fetal resorptions, and pregnancy disruptions. In rats, dose-related embryo/fetal toxicity and postnatal developmental toxicity were observed in offspring resulting from parents treated with omeprazole at 13.8 to 138.0 mg/kg/day (about 3.4 to 34 times an oral human dose of 40 mg on a body surface area basis), administered prior to mating through the lactation period.

Esomeprazole

No effects on embryo-fetal development were observed in reproduction studies with esomeprazole magnesium in rats at oral doses up to 280 mg/kg/day (about 68 times an oral human dose of 40 mg on a body surface area basis) or in rabbits at oral doses up to 86 mg/kg/day (about 41 times an oral human dose of 40 mg on a body surface area basis) administered during organogenesis.

A pre- and postnatal developmental toxicity study in rats with additional endpoints to evaluate bone development was performed with esomeprazole magnesium at oral doses of 14 to 280 mg/kg/day (about 3.4 to 68 times an oral human dose of 40 mg on a body surface area basis). Neonatal/early postnatal (birth to weaning) survival was decreased at doses equal to or greater than 138 mg/kg/day (about 34 times an oral human dose of 40 mg on a body surface area basis). Body weight and body weight gain were reduced and neurobehavioral or general developmental delays in the immediate post-weaning timeframe were evident at doses equal to or greater than 69 mg/kg/day (about 17 times an oral human dose of 40 mg on a body surface area basis). In addition, decreased femur length, width and thickness of cortical bone, decreased thickness of the tibial growth plate and minimal to mild bone marrow hypocellularity were noted at doses equal to or greater than 14 mg/kg/day (about 3.4 times an oral human dose of 40 mg on a body surface area basis). Physeal dysplasia in the femur was observed in offspring of rats treated with oral doses of esomeprazole magnesium at doses equal to or greater than 138 mg/kg/day (about 34 times an oral human dose of 40 mg on a body surface area basis).

Effects on maternal bone were observed in pregnant and lactating rats in a pre- and postnatal toxicity study when esomeprazole magnesium was administered at oral doses of 14 to 280 mg/kg/day (about 3.4 to 68 times an oral human dose of 40 mg on a body surface area basis). When rats were dosed from gestational day 7 through weaning on postnatal day 21, a statistically significant decrease in maternal femur weight of up to 14% (as compared to placebo treatment) was observed at doses equal to or greater than 138 mg/kg/day (about 34 times an oral human dose of 40 mg on a body surface area basis).

A pre- and postnatal development study in rats with esomeprazole strontium (using equimolar doses compared to esomeprazole magnesium study) produced similar results in dams and pups as described above.

A follow up developmental toxicity study in rats with further time points to evaluate pup bone development from postnatal day 2 to adulthood was performed with esomeprazole magnesium at oral doses of 280 mg/kg/day (about 68 times an oral human dose of 40 mg on a body surface area basis) where esomeprazole administration was from either gestational day 7 or gestational day 16 until parturition. When maternal administration was confined to gestation only, there were no effects on bone physeal morphology in the offspring at any age.

8.2 Lactation

Risk Summary

Esomeprazole is the S-isomer of omeprazole and limited data suggest that omeprazole may be present in human milk. There are no clinical data on the effects of esomeprazole on the breastfed infant or on milk production. The developmental and health benefits of breastfeeding should be considered along with the mother’s clinical need for NEXIUM and any potential adverse effects on the breastfed infant from NEXIUM or from the underlying maternal condition.

8.4 Pediatric Use

Healing of EE

Pediatric Patients 1 Year to 17 Years of Age

The safety and effectiveness of NEXIUM delayed-release capsules and NEXIUM for delayed-release oral suspension have been established in pediatric patients 12 years to 17 years for short-term treatment (4 to 8 weeks) for healing of EE. The safety and effectiveness of NEXIUM for delayed-release oral suspension have been established in pediatric patients 1 year to 11 years for short-term treatment (up to 8 weeks) for healing of EE. Use of NEXIUM for this indication is supported by evidence from adequate and well-controlled studies in adults with additional safety and pharmacokinetic data in pediatric patients 1 year to 17 years of age. The safety profile in pediatric patients 1 year to 17 years of age was similar to adults [see Adverse Reactions (6.1), Clinical Pharmacology (12.3), Clinical Studies (14.4)].

Pediatric Patients 1 Month to Less Than 1 Year of Age

The safety and effectiveness of NEXIUM for delayed-release oral suspension have been established in pediatric patients 1 month to less than 1 year of age for short-term treatment (up to 6 weeks) of EE due to acid-mediated GERD. Use of NEXIUM for this indication is supported by evidence from adequate and well-controlled studies in adults with additional safety, pharmacokinetic, and pharmacodynamic data in pediatric patients 1 month to less than 1 year of age. The safety profile in pediatric patients 1 month to less than 1 year of age was similar to adults [see Adverse Reactions (6.1), Clinical Pharmacology (12.2, 12.3)].

The safety and effectiveness of NEXIUM for the treatment of EE due to acid-mediated GERD in pediatric patients less than 1 month of age have not been established.

Symptomatic GERD

Pediatric Patients 1 Year to 17 Years of Age

The safety and effectiveness of NEXIUM delayed-release capsules and NEXIUM for delayed-release oral suspension have been established in pediatric patients 12 years to 17 years of age for the short-term treatment (4 weeks) of heartburn and other symptoms associated with GERD. The safety and effectiveness of NEXIUM for delayed-release oral suspension have been established in pediatric patients 1 year to 11 years of age for the short-term treatment (up to 8 weeks) of heartburn and other symptoms associated with GERD. Use of NEXIUM for this indication is supported by evidence from adequate and well-controlled studies in adults with additional safety and pharmacokinetic data in pediatric patients 1 year to 17 years of age. The safety profile in pediatric patients 1 year to 17 years of age was similar to adults [see Adverse Reactions (6.1), Clinical Pharmacology (12.3), Clinical Studies (14.4)].

The safety and effectiveness of NEXIUM for the treatment of symptomatic GERD in pediatric patients less than 1 year of age have not been established.

Infants 1 Month to Less Than 1 Year of Age

NEXIUM was not found to be effective in a multicenter, randomized, double-blind, controlled, treatment-withdrawal study of 98 infants aged 1 month to 11 months for the treatment of symptomatic GERD. Patients were enrolled if they had either a clinical diagnosis of suspected GERD, symptomatic GERD, or endoscopically proven GERD. Twenty of 98 enrolled patients underwent endoscopy, and 6 patients were found to have EE on endoscopy at baseline. All patients received NEXIUM for delayed-release oral suspension once daily during a two-week, open-label phase of the study. There were 80 patients who attained a pre-specified level of symptom improvement and who entered the double-blind phase, in which they were randomized in equal proportions to receive NEXIUM or placebo for the next four weeks. Efficacy was assessed by observing the time from randomization to study discontinuation due to symptom worsening during the four-week, treatment-withdrawal phase. There was no statistically significant difference between NEXIUM and placebo in the rate of discontinuation due to symptom worsening; therefore, these results do not support the use of NEXIUM for the treatment of symptomatic GERD in infants 1 month to less than 1 year of age.

Other Conditions

The safety and effectiveness of NEXIUM for the risk reduction of NSAID-associated gastric ulcer, H. pylori eradication to reduce the risk of duodenal ulcer recurrence and treatment of pathological hypersecretory conditions have not been established in pediatric patients.

Juvenile Animal Toxicity Studies

In a juvenile rat toxicity study, esomeprazole was administered with both magnesium and strontium salts at oral doses about 34 to 68 times a daily human dose of 40 mg based on body surface area. Increases in death were seen at the high dose, and at all doses of esomeprazole, there were decreases in body weight, body weight gain, femur weight and femur length, and decreases in overall growth [see Nonclinical Toxicology (13.2)].

8.5 Geriatric Use

Of the total number of patients who received NEXIUM in clinical trials, 1459 were 65 to 74 years of age and 354 patients were 75 years of age and older.

No overall differences in safety and efficacy were observed between the elderly and younger individuals, and other reported clinical experience has not identified differences in responses between elderly and younger patients, but greater sensitivity of some older individuals cannot be ruled out.

8.6 Hepatic Impairment

In patients with severe hepatic impairment (Child-Pugh Class C) exposure to esomeprazole substantially increased compared to healthy subjects. Dosage modification of NEXIUM is recommended for patients with severe hepatic impairment for the healing of EE, risk reduction of NSAID-associated gastric ulcer, H. pylori eradication to reduce the risk of duodenal ulcer recurrence, and pathological hypersecretory conditions including Zollinger-Ellison Syndrome [see Dosage and Administration (2.1), Clinical Pharmacology (12.3)].

In patients with mild to moderate liver impairment (Child-Pugh Classes A and B), no dosage adjustment is necessary.

10 OVERDOSAGE

Manifestations in patients exposed to omeprazole, the racemic mixture, at doses up to 2,400 mg (120 times the usual recommended clinical dose) include confusion, drowsiness, blurred vision, tachycardia, nausea, diaphoresis, flushing, headache, dry mouth, and other adverse reactions similar to those seen at recommended dosages. See the full prescribing information for omeprazole for complete safety information. No specific antidote for esomeprazole is known. Since esomeprazole is extensively protein bound, it is not expected to be removed by dialysis. In the event of overdosage, treatment should be symptomatic and supportive.

If over-exposure occurs, call your Poison Control Center at 1-800-222-1222 for current information on the management of poisoning or overdosage.

11 DESCRIPTION

The active ingredient in NEXIUM® (esomeprazole magnesium) delayed-release capsules for oral administration and NEXIUM (esomeprazole magnesium) for delayed-release oral suspension is bis(5-methoxy-2-[(S)-[(4-methoxy-3,5-dimethyl-2-pyridinyl)methyl]sulfinyl]-1H-benzimidazole-1-yl) magnesium trihydrate, a PPI. Esomeprazole is the S-isomer of omeprazole, which is a mixture of the S- and R- isomers. (Initial U.S. approval of esomeprazole magnesium: 2001). Its molecular formula is (C17H18N3O3S)2Mg x 3 H2O with molecular weight of 767.2 as a trihydrate and 713.1 on an anhydrous basis. The structural formula is:

The magnesium salt is a white to slightly colored crystalline powder. It contains 3 moles of water of solvation and is slightly soluble in water. The stability of esomeprazole magnesium is a function of pH; it rapidly degrades in acidic media, but it has acceptable stability under alkaline conditions. At pH 6.8 (buffer), the half-life of the magnesium salt is about 19 hours at 25°C and about 8 hours at 37°C.

NEXIUM is supplied in delayed-release capsules and in packets for a delayed-release oral suspension. Each NEXIUM delayed-release capsule contains 20 mg of esomeprazole (equivalent to 22.3 mg esomeprazole magnesium trihydrate) or 40 mg of esomeprazole (equivalent to 44.5 mg esomeprazole magnesium trihydrate) in the form of enteric-coated granules with the following inactive ingredients: glyceryl monostearate 40-55, hydroxypropyl cellulose, hypromellose, magnesium stearate, methacrylic acid copolymer type C, polysorbate 80, sugar spheres, talc, and triethyl citrate. The capsule shells have the following inactive ingredients: D&C Red #28, D&C Yellow #10, ethyl alcohol, FD&C Blue #1, FD&C Red #40, gelatin, isopropyl alcohol, n-butyl alcohol, polyvinyl pyrrolidone, propylene glycol, shellac, sodium hydroxide, and titanium dioxide.

Each packet of NEXIUM for delayed-release oral suspension contains esomeprazole, in the form of same enteric-coated granules used in NEXIUM delayed-release capsules, and also inactive granules:

- 2.5 mg esomeprazole (equivalent to 2.8 mg esomeprazole magnesium trihydrate)
- 5 mg esomeprazole (equivalent to 5.6 mg esomeprazole magnesium trihydrate)
- 10 mg esomeprazole (equivalent to 11.1 mg esomeprazole magnesium trihydrate)
- 20 mg esomeprazole (equivalent to 22.3 mg esomeprazole magnesium trihydrate)
- 40 mg esomeprazole (equivalent to 44.5 mg esomeprazole magnesium trihydrate)

The inactive granules are composed of the following ingredients: citric acid, crospovidone, dextrose, hydroxypropyl cellulose, iron oxide, and xanthan gum. The esomeprazole granules and inactive granules are constituted with water to form a suspension and are given by oral, nasogastric, or gastric administration.

12 CLINICAL PHARMACOLOGY

12.1 Mechanism of Action

Esomeprazole belongs to a class of antisecretory compounds, the substituted benzimidazoles, that suppress gastric acid secretion by specific inhibition of the H+/K+ ATPase enzyme system at the secretory surface of the gastric parietal cell. Esomeprazole is protonated and converted in the acidic compartment of the parietal cell forming the active inhibitor, the achiral sulphenamide. Because this enzyme system is regarded as the acid (proton) pump within the gastric mucosa, esomeprazole has been characterized as a gastric acid-pump inhibitor, in that it blocks the final step of acid production. This effect is dose-related and leads to inhibition of both basal and stimulated acid secretion irrespective of the stimulus.

12.2 Pharmacodynamics

Antisecretory Activity

Adults

The effect of esomeprazole on intragastric pH was determined in adult patients with symptomatic GERD in two separate studies. In the first study of 36 patients, NEXIUM 40 mg and 20 mg delayed-release capsules were administered once daily over 5 days as shown in Table 5:

Table 5: Effect of Esomeprazole on Intragastric pH on Day 5 (N=36) Following Once Daily Dosing of NEXIUM Delayed-Release Capsules in Adult Patients with Symptomatic GERD
Parameter | NEXIUM Delayed-Release Capsules
Parameter | 40 mg once daily | 20 mg once daily
% Time Gastric pH >4 [Gastric pH was measured over a 24-hour period] (Hours) | 70% [p< 0.01 NEXIUM 40 mg vs. NEXIUM 20 mg]; (16.8 h) | 53%; (12.7 h)
Coefficient of variation | 26% | 37%
Median 24 Hour pH | 4.9 | 4.1
Coefficient of variation | 16% | 27%

In a second study, the effect on intragastric pH of NEXIUM 40 mg delayed-release capsules administered once daily over a five-day period was similar to the first study, (% time with pH > 4 was 68% or 16.3 hours).

Pediatrics

In infants (1 to 11 months old, inclusive) with GERD given NEXIUM for delayed-release oral suspension 1 mg/kg once daily, the percent time with intragastric pH > 4 increased from 29% at baseline to 69% on Day 7, which is similar to the pharmacodynamic effect in adults.

Serum Gastrin Effects

The effect of esomeprazole on serum gastrin concentrations was evaluated in approximately 2,700 patients in clinical trials of oral esomeprazole for up to 8 weeks and in over 1,300 patients for up to 12 months. The mean fasting gastrin level increased in a dose-related manner. The increase in serum gastrin concentrations reached a plateau within two to three months of therapy and returned to baseline levels within four weeks after discontinuation of therapy.

Increased gastrin causes enterochromaffin-like cell hyperplasia and increased serum Chromogranin A (CgA) levels. The increased CgA levels may cause false positive results in diagnostic investigations for neuroendocrine tumors [see Warnings and Precautions (5.11)]

Enterochromaffin-like (ECL) Cell Effects

Human gastric biopsy specimens have been obtained from more than 3,000 patients (both pediatrics and adults) treated with omeprazole in long-term clinical trials. The incidence of ECL cell hyperplasia in these studies increased with time; however, no case of ECL cell carcinoids, dysplasia, or neoplasia has been found in these patients [see Nonclinical Toxicology (13.1)]

In over 1,000 patients treated with oral esomeprazole (10 mg, 20 mg or 40 mg/day) for up to 12 months, the prevalence of ECL cell hyperplasia increased with time and dose. No patient developed ECL cell carcinoids, dysplasia, or neoplasia in the gastric mucosa.

Endocrine Effects

Esomeprazole had no effect on thyroid function in adults when given NEXIUM 20 mg or 40 mg delayed-release capsules once daily for 4 weeks. Other effects of esomeprazole on the endocrine system were assessed in studies of omeprazole. Oral doses of omeprazole 30 mg or 40 mg once daily for 2 to 4 weeks had no effect on carbohydrate metabolism, circulating levels of parathyroid hormone, cortisol, estradiol, testosterone, prolactin, cholecystokinin, or secretin.

12.3 Pharmacokinetics

Absorption

NEXIUM delayed-release capsules and NEXIUM for delayed-release oral suspension. showed similar bioavailability after a single dose (40 mg) administration in 94 healthy male and female subjects under fasting conditions. After oral administration, peak plasma levels (Cmax) of esomeprazole occur at approximately 1.5 hours (Tmax). The Cmax increases proportionally when the dose is increased, and there is a three-fold increase in the area under the plasma concentration-time curve (AUC) from 20 to 40 mg. At repeated once-daily dosing with 40 mg, the systemic bioavailability is approximately 90% compared to 64% after a single dose of 40 mg. The mean exposure (AUC) to esomeprazole increases from 4.32 micromol*hr/L on Day 1 to 11.2 micromol*hr/L on Day 5 after 40 mg once daily dosing.

The AUC after administration of a single 40 mg dose of NEXIUM delayed-release capsules is decreased by 43% to 53% after food intake compared to fasting conditions [see Dosage and Administration (2.3)]. The pharmacokinetics of esomeprazole in adult patients with symptomatic GERD following repeated once daily administration of 20 mg and 40 mg NEXIUM delayed-release capsules over a period of five days are shown in Table 6:

Table 6: Geometric Mean (95% CI) Pharmacokinetic Parameters of Esomeprazole on Day 5 Following Once Daily Dosing of NEXIUM Delayed-Release Capsules in Adult Patients with Symptomatic GERD
 | NEXIUM delayed-release capsules
Parameter [Values represent the geometric mean, except the Tmax, which is the arithmetic mean; CV = Coefficient of variation] (CV) | 40 mg once daily; (n=36) | 20 mg once daily; (n=36)
AUC (micromol·h/L) | 12.6 (42%) | 4.2 (59%)
Cmax (micromol/L) | 4.7 (37%) | 2.1 (45%)
Tmax (hours) | 1.6 | 1.6
t1/2 (hours) | 1.5 | 1.2

Esomeprazole is a time-dependent inhibitor of CYP2C19, resulting in autoinhibition and nonlinear pharmacokinetics. The systemic exposure increases in a more than dose proportional manner after multiple oral doses of esomeprazole. Compared to the first dose, the systemic exposure (Cmax and AUC0-24h) at steady state following once a day dosing increased by 43% and 90%, respectively, compared to after the first dose for the 20 mg dose and increased by 95% and 159%, respectively, for the 40 mg dose.

Distribution

Esomeprazole is 97% bound to plasma proteins. Plasma protein binding is constant over the concentration range of 2 to 20 micromol/L. The apparent volume of distribution at steady state in healthy subjects is approximately 16 L.

Elimination

Metabolism

Esomeprazole is extensively metabolized in the liver by the cytochrome P450 (CYP) enzyme system. The metabolites of esomeprazole lack antisecretory activity. The major part of esomeprazole’s metabolism is dependent upon the CYP2C19 isoenzyme, which forms the hydroxy and desmethyl metabolites. The remaining amount is dependent on CYP3A4 which forms the sulphone metabolite.

Excretion

The plasma elimination half-life of esomeprazole is approximately 1 to 1.5 hours. Less than 1% of parent drug is excreted in the urine. Approximately 80% of an oral dose of esomeprazole is excreted as inactive metabolites in the urine, and the remainder is found as inactive metabolites in the feces.

Combination Therapy with Amoxicillin and Clarithromycin

NEXIUM delayed-release capsules 40 mg once daily was given in combination with amoxicillin 1000 mg twice daily and clarithromycin 500 mg twice daily for 7 days to 17 healthy male and female subjects. The mean steady state AUC and Cmax of esomeprazole increased by 70% and 18%, respectively during combination therapy compared to treatment with NEXIUM alone. The observed increase in esomeprazole exposure during co-administration with amoxicillin and clarithromycin is not expected to be clinically relevant.

The pharmacokinetic parameters for amoxicillin and clarithromycin were similar during combination therapy and administration of each drug alone. However, the mean AUC and Cmax for 14-hydroxyclarithromycin increased by 19% and 22%, respectively, during combination therapy compared to treatment with clarithromycin alone. This increase in exposure to 14-hydroxyclarithromycin is not considered to be clinically relevant.

Specific Populations

Geriatric Patients

The AUC and Cmax values of esomeprazole were slightly higher (25% and 18%, respectively) in the elderly as compared to younger subjects at steady state. This increase in exposure is not considered clinically relevant.

Pediatric Patients

1 Month to 11 Months of Age

The pharmacokinetic parameters following repeated dose administration of esomeprazole magnesium 1 mg/kg once daily for 7 to 8 days in 1 month to 11-month-old infants with GERD are summarized in Table 7.

Table 7: Summary of Esomeprazole Pharmacokinetic Parameters Following Once Daily Dosing of Oral Esomeprazole Magnesium for 7 to 8 Days in 1 Month to 1 Year Old Infants with GERD
Parameter | Esomeprazole Magnesium 1 mg/kg Orally Once Daily
AUC (micromol·h/L) (n=7) [Geometric mean] | 3.51
Css, max (micromol/L) (n=15) | 0.87
t½ (h) (n=8) | 0.93
tmax (h) (n=15) [Median] | 3.0

Subsequent pharmacokinetic simulation analyses showed that for pediatric patients 1 month to 11 months of age, a dosage regimen of 2.5 mg once daily (body weight 3 to 5 kg), 5 mg once daily (body weight more than 5 to 7.5 kg) and 10 mg once daily for (body weight more than 7.5 to 12 kg) would achieve comparable steady-state plasma exposures (AUC) to that observed with 10 mg once daily in patients 1 year to 11 year of age and 20 mg once daily in patients 12 years to 18 years of age, as well as adults.

Apparent clearance (CL/F) increases with age in pediatric patients with GERD from 1 month to 2 years of age.

1 Year to 11 Years of Age

The pharmacokinetics of esomeprazole were studied in pediatric patients with GERD aged 1 year to 11 years. Following once daily dosing with NEXIUM for delayed-release oral suspension for 5 days, the total exposure (AUC) for the 10 mg dosage in patients aged 6 years to 11 years was similar to that seen with the 20 mg dosage in adults and adolescents aged 12 years to 17 years. The total exposure for the 10 mg dosage in patients aged 1 year to 5 years was approximately 30% higher than the 10 mg dosage in patients aged 6 years to 11 years. The total exposure for the 20 mg dosage in patients aged 6 years to 11 years was higher than that observed with the 20 mg dosage in patients aged 12 years to 17 years and adults, but lower than that observed with the 40 mg dosage in 12 to 17 year-olds and adults. See Table 8.

Table 8: Summary of Esomeprazole Pharmacokinetic Parameters Following Once Daily Dosing of NEXIUM for Delayed-Release Oral Suspension for 5 Days in 1 Year to 11 Year Old Patients with GERD
Parameter | NEXIUM For Delayed-Release Oral Suspension
Parameter | 1 Year to 5 Years | 6 Years to 11 Years
Parameter | 10 mg once daily (N=8) | 10 mg once daily (N=7) | 20 mg once daily (N=6)
AUC (micromol h/L) [Geometric mean] | 4.83 | 3.70 | 6.28
Cmax (micromol/L) | 2.98 | 1.77 | 3.73
tmax (h) [Arithmetic mean] | 1.44 | 1.79 | 1.75
t½λz (h) | 0.74 | 0.88 | 0.73
Cl/F (L/h) | 5.99 | 7.84 | 9.22

12 Years to 17 Years of Age

The pharmacokinetics of NEXIUM were studied in 28 adolescent patients with GERD aged 12 to 17 years inclusive, in a single center study. Patients were randomized to receive NEXIUM 20 mg or 40 mg once daily for 8 days. Mean Cmax and AUC values of esomeprazole were not affected by body weight or age; and more than dose-proportional increases in mean Cmax and AUC values were observed between the two dose groups in the study. Overall, NEXIUM pharmacokinetics in adolescent patients aged 12 to 17 years were similar to those observed in adult patients with symptomatic GERD. See Table 9.

Table 9: Comparison of Esomeprazole Pharmacokinetic Parameters Following Once Daily Dosing of NEXIUM Delayed-Release Capsules in Pediatric Patients 12 Years to 17 Years with GERD and Adults with Symptomatic GERD [Data obtained from two independent studies.]
Parameter | NEXIUM Delayed-Release Capsules
Parameter | 12 Years to 17 Years (N=28) |  | Adults (N=36)
Parameter | 20 mg once daily; for 8 days | 40 mg once daily; for 8 days | 20 mg once daily; for 5 days | 40 mg once daily; for 5 days
AUC (micromol h/L) | 3.65 | 13.86 | 4.2 | 12.6
Cmax (micromol/L) | 1.45 | 5.13 | 2.1 | 4.7
tmax (h) | 2.00 | 1.75 | 1.6 | 1.6
t½λz (h) | 0.82 | 1.22 | 1.2 | 1.5
Data presented are geometric means for AUC, Cmax and t½λz, and median value for tmax.

Male and Female Patients

The AUC and Cmax values of esomeprazole were slightly higher (13%) in females than in males at steady state when dosed orally. This increase in exposure is not considered clinically relevant.

Patients with Renal Impairment

The pharmacokinetics of NEXIUM in patients with renal impairment are not expected to be altered relative to healthy subjects as less than 1% of esomeprazole is excreted unchanged in urine.

Patients with Hepatic Impairment

The steady state pharmacokinetics of esomeprazole obtained after administration of NEXIUM delayed-release capsules 40 mg orally once daily to patients with mild (Child-Pugh Class A, n=4), moderate (Child-Pugh Class B, n=4), and severe (Child-Pugh Class C, n=4) hepatic impairment were compared to those obtained in 36 male and female GERD patients with normal liver function. In patients with mild and moderate hepatic impairment, the AUCs were within the range that could be expected in patients with normal liver function. In patients with severe hepatic impairment the AUCs were 2 to 3 times higher than in the patients with normal liver function [see Use in Specific Populations (8.6)].

Drug Interaction Studies

Effect of Esomeprazole/Omeprazole on Other Drugs

In vitro and in vivo studies have shown that esomeprazole is not likely to inhibit CYPs 1A2, 2A6, 2C9, 2D6, 2E1 and 3A4.

Antiretrovirals

For some antiretroviral drugs, such as rilpivirine, atazanavir and nelfinavir, decreased serum concentrations have been reported when given together with omeprazole [see Drug Interactions (7)].

Rilpivirine:

Following multiple doses of rilpivirine (150 mg, daily) and omeprazole (20 mg, daily), AUC was decreased by 40%, Cmax by 40%, and Cmin by 33% for rilpivirine [see Contraindications (4)].

Nelfinavir:

Following multiple doses of nelfinavir (1250 mg, twice daily) and omeprazole (40 mg daily), AUC was decreased by 36% and 92%, Cmax by 37% and 89% and Cmin by 39% and 75% respectively for nelfinavir and M8.

Atazanavir:

Following multiple doses of atazanavir (400 mg, daily) and omeprazole (40 mg, daily, 2 hours before atazanavir), AUC was decreased by 94%, Cmax by 96%, and Cmin by 95%.

Saquinavir:

Following multiple dosing of saquinavir/ritonavir (1000/100 mg) twice daily for 15 days with omeprazole 40 mg daily co-administered days 11 to 15. The AUC was increased by 82%, Cmax by 75%, and Cmin by 106%. The mechanism behind this interaction is not fully elucidated.

Clopidogrel

In a crossover study, healthy subjects were administered clopidogrel (300 mg loading dose followed by 75 mg per day as the maintenance dosage for 28 days) alone and with esomeprazole (40 mg orally once daily at the same time as clopidogrel) for 29 days. Exposure to the active metabolite of clopidogrel was reduced by 35% to 40% over this time period when clopidogrel and esomeprazole were administered together. Pharmacodynamic parameters were also measured and demonstrated that the change in inhibition of platelet aggregation was related to the change in the exposure to clopidogrel active metabolite [see Warnings and Precautions (5.7) and Drug Interactions (7)].

Mycophenolate Mofetil

Administration of omeprazole 20 mg twice daily for 4 days and a single 1000 mg dose of MMF approximately one hour after the last dose of omeprazole to 12 healthy subjects in a cross-over study resulted in a 52% reduction in the Cmax and 23% reduction in the AUC of MPA [see Drug Interactions (7)].

Cilostazol

Omeprazole acts as an inhibitor of CYP2C19. Omeprazole, given in doses of 40 mg daily for one week to 20 healthy subjects in cross-over study, increased Cmax and AUC of cilostazol by 18% and 26% respectively. The Cmax and AUC of one of the active metabolites, 3,4-dihydro-cilostazol, which has 4 to 7 times the activity of cilostazol, were increased by 29% and 69%, respectively. Co-administration of cilostazol with omeprazole is expected to increase concentrations of cilostazol and the above mentioned active metabolite [see Drug Interactions (7)].

Diazepam

Co-administration of esomeprazole 30 mg and diazepam, a CYP2C19 substrate, resulted in a 45% decrease in clearance of diazepam. Increased plasma levels of diazepam were observed 12 hours after dosing and onwards. However, at that time, the plasma levels of diazepam were below the therapeutic interval, and thus this interaction is unlikely to be of clinical relevance.

Digoxin

Concomitant administration of omeprazole 20 mg once daily and digoxin in healthy subjects increased the bioavailability of digoxin by 10% (30% in two subjects) [see Drug Interactions (7)].

Other Drugs

Concomitant administration of esomeprazole and either naproxen (non-selective NSAID) did not identify any clinically relevant changes in the pharmacokinetic profiles of these NSAIDs.

Effect of Other Drugs on Esomeprazole/Omeprazole

St. John’s Wort

In a cross-over study in 12 healthy male subjects, St. John’s Wort (300 mg three times daily for 14 days) significantly decreased the systemic exposure of omeprazole in CYP2C19 poor metabolizers (Cmax and AUC both decreased by 38%) and extensive metabolizers (Cmax and AUC decreased by 50% and 44%, respectively) [see Drug Interactions (7)].

Voriconazole

Concomitant administration of omeprazole and voriconazole (a combined inhibitor of CYP2C19 and CYP3A4) resulted in more than doubling of the omeprazole exposure. When voriconazole (400 mg every 12 hours for one day, followed by 200 mg once daily for 6 days) was given with omeprazole (40 mg once daily for 7 days) to healthy subjects, the steady-state Cmax and AUC0-24 of omeprazole significantly increased: an average of 2 times (90% CI: 1.8, 2.6) and 4 times (90% CI: 3.3, 4.4), respectively, as compared to when omeprazole was given without voriconazole [see Drug Interactions (7)].

Other Drugs

Co-administration of esomeprazole with oral contraceptives, diazepam, phenytoin, quinidine, naproxen (non-selective NSAID) did not seem to change the pharmacokinetic profile of esomeprazole.

12.4 Microbiology

NEXIUM, amoxicillin, and clarithromycin triple therapy has been shown to be active against most strains of Helicobacter pylori (H. pylori) in vitro and in clinical infections [see Indications and Usage (1) and Clinical Studies (14)].

Helicobacter pylori: Susceptibility testing of H. pylori isolates was performed for amoxicillin and clarithromycin using agar dilution methodology, and minimum inhibitory concentrations (MICs) were determined.

Pretreatment Resistance: Clarithromycin pretreatment resistance rate (MIC ≥ 1 mcg/mL) to H. pylori was 15% (66/445) at baseline in all treatment groups combined. A total of > 99% (394/395) of patients had H. pylori isolates that were considered to be susceptible (MIC ≤ 0.25 mcg/mL) to amoxicillin at baseline. One patient had a baseline H. pylori isolate with an amoxicillin MIC = 0.5 mcg/mL.

Clarithromycin Susceptibility Test Results and Clinical/Bacteriologic Outcomes: The baseline H. pylori clarithromycin susceptibility results and the H. pylori eradication results at the Day 38 visit are shown in Table 10:

Table 10: Clarithromycin Susceptibility Test Results and Clinical/Bacteriological Outcomes [Includes only patients with pretreatment and post-treatment clarithromycin susceptibility test results] for Triple Therapy (NEXIUM Delayed-Release Capsules 40 mg once daily, Amoxicillin 1000 mg twice daily and Clarithromycin 500 mg twice daily for 10 days)
Clarithromycin; Pretreatment Results |  | H. pylori negative; (Eradicated) | H. pylori positive; (Not Eradicated); Post-treatment susceptibility results
 |  |  | S [Susceptible (S) MIC ≤ 0.25 mcg/mL, Intermediate (I) MIC = 0.5 mcg/mL, Resistant (R) MIC ≥ 1.0 mcg/mL] | I | R | No MIC
Susceptible | 182 | 162 | 4 | 0 | 2 | 14
Intermediate | 1 | 1 | 0 | 0 | 0 | 0
Resistant | 29 | 13 | 1 | 0 | 13 | 2

Patients not eradicated of H. pylori following triple therapy with NEXIUM, amoxicillin and clarithromycin will likely have clarithromycin resistant H. pylori isolates. Therefore, clarithromycin susceptibility testing should be done, when possible. Patients with clarithromycin resistant H. pylori should not be re-treated with a clarithromycin-containing regimen.

Amoxicillin Susceptibility Test Results and Clinical/Bacteriological Outcomes:

In patients treated with NEXIUM, amoxicillin and clarithromycin in clinical trials, 83% (176/212) of the patients who had pretreatment amoxicillin susceptible MICs (≤ 0.25 mcg/mL) were eradicated of H. pylori, and 17% (36/212) were not eradicated of H. pylori. Of the 36 patients who were not eradicated of H. pylori, 16 had no post-treatment susceptibility test results and 20 had post-treatment H. pylori isolates with amoxicillin susceptible MICs. Fifteen of the patients who were not eradicated of H. pylori also had post-treatment H. pylori isolates with clarithromycin resistant MICs. There were no patients with H. pylori isolates who developed treatment emergent resistance to amoxicillin.

Susceptibility Test for Helicobacter pylori: For susceptibility testing information about Helicobacter pylori, see Microbiology section in prescribing information for clarithromycin and amoxicillin.

Effects on Gastrointestinal Microbial Ecology: Decreased gastric acidity due to any means, including proton pump inhibitors, increases gastric counts of bacteria normally present in the gastrointestinal tract. Treatment with PPIs may lead to slightly increased risk of gastrointestinal infections such as Salmonella and Campylobacter and possibly Clostridium difficile in hospitalized patients.

12.5 Pharmacogenomics

CYP2C19, a polymorphic enzyme, is involved in the metabolism of esomeprazole. The CYP2C19*1 allele is fully functional while the CYP2C19*2 and *3 alleles are nonfunctional. There are other alleles associated with no or reduced enzymatic function. Patients carrying two fully functional alleles are extensive metabolizers and those carrying two loss-of-function alleles are poor metabolizers. The systemic exposure to esomeprazole varies with a patient’s metabolism status: poor metabolizers > intermediate metabolizers > extensive metabolizers. Approximately 3% of Caucasians and 15 to 20% of Asians are CYP2C19 poor metabolizers.

Systemic esomeprazole exposures were modestly higher (approximately 17%) in CYP2C19 intermediate metabolizers (IM; n=6) compared to extensive metabolizers (EM; n=17) of CYP2C19. Similar pharmacokinetic differences were noted across these genotypes in a study of Chinese healthy subjects that included 7 EMs and 11 IMs. There is very limited pharmacokinetic information for poor metabolizers (PM) from these studies.

At steady state following once daily administration of esomeprazole 40 mg, the ratio of AUC in poor metabolizers to AUC in the rest of the population (EMs) is approximately 1.5. This change in exposure is not considered clinically meaningful.

13 NONCLINICAL TOXICOLOGY

13.1 Carcinogenesis, Mutagenesis, Impairment of Fertility

The carcinogenic potential of NEXIUM was assessed using studies of omeprazole, of which esomeprazole is an enantiomer. In two 24-month oral carcinogenicity studies in rats, omeprazole at daily doses of 1.7, 3.4, 13.8, 44, and 140.8 mg/kg/day (about 0.4 to 34 times the human dose of 40 mg/day expressed on a body surface area basis) produced gastric ECL cell carcinoids in a dose-related manner in both male and female rats; the incidence of this effect was markedly higher in female rats, which had higher blood levels of omeprazole. Gastric carcinoids seldom occur in the untreated rat. In addition, ECL cell hyperplasia was present in all treated groups of both sexes. In one of these studies, female rats were treated with 13.8 mg omeprazole/kg/day (about 3.4 times the human dose of 40 mg/day on a body surface area basis) for 1 year, then followed for an additional year without the drug. No carcinoids were seen in these rats. An increased incidence of treatment-related ECL cell hyperplasia was observed at the end of 1 year (94% treated vs. 10% controls). By the second year the difference between treated and control rats was much smaller (46% vs. 26%) but still showed more hyperplasia in the treated group. Gastric adenocarcinoma was seen in one rat (2%). No similar tumor was seen in male or female rats treated for 2 years. For this strain of rat no similar tumor has been noted historically, but a finding involving only one tumor is difficult to interpret. A 78-week mouse carcinogenicity study of omeprazole did not show increased tumor occurrence, but the study was not conclusive.

Esomeprazole was negative in the Ames mutation test, in the in vivo rat bone marrow cell chromosome aberration test, and the in vivo mouse micronucleus test. Esomeprazole, however, was positive in the in vitro human lymphocyte chromosome aberration test. Omeprazole was positive in the in vitro human lymphocyte chromosome aberration test, the in vivo mouse bone marrow cell chromosome aberration test, and the in vivo mouse micronucleus test.

The potential effects of esomeprazole on fertility and reproductive performance were assessed using omeprazole studies. Omeprazole at oral doses up to 138 mg/kg/day in rats (about 34 times the human dose of 40 mg/day on a body surface area basis) was found to have no effect on reproductive performance of parental animals.

13.2 Animal Toxicology and/or Pharmacology

Reproduction Studies

Reproduction studies have been performed in rats at oral doses up to 280 mg/kg/day (about 68 times an oral human dose of 40 mg on a body surface area basis) and in rabbits at oral doses up to 86 mg/kg/day (about 42 times an oral human dose of 40 mg on a body surface area basis) and have revealed no evidence of impaired fertility or harm to the fetus due to esomeprazole [see Use in Specific Populations (8.1)].

Juvenile Animal Study

A 28-day toxicity study with a 14-day recovery phase was conducted in juvenile rats with esomeprazole magnesium at doses of 70 to 280 mg /kg/day (about 17 to 68 times a daily oral human dose of 40 mg on a body surface area basis). An increase in the number of deaths at the high dose of 280 mg/kg/day was observed when juvenile rats were administered esomeprazole magnesium from postnatal day 7 through postnatal day 35. In addition, doses equal to or greater than 140 mg/kg/day (about 34 times a daily oral human dose of 40 mg on a body surface area basis), produced treatment-related decreases in body weight (approximately 14%) and body weight gain, decreases in femur weight and femur length, and affected overall growth. Comparable findings described above have also been observed in this study with another esomeprazole salt, esomeprazole strontium, at equimolar doses of esomeprazole.

14 CLINICAL STUDIES

14.1 Healing of EE in Adults

The healing rates of NEXIUM delayed-release capsules 40 mg, NEXIUM delayed-release capsules 20 mg, and omeprazole delayed-release capsules 20 mg (the approved dose for this indication) once daily were evaluated in adult patients with endoscopically diagnosed EE in four multicenter, double-blind, randomized studies. The healing rates at Weeks 4 and 8 were evaluated and are shown in Table 11:

Table 11: EE Healing Rate (Life-Table Analysis) in Adults with EE Treated with NEXIUM Delayed-Release Capsules or Omeprazole Delayed-Release Capsules Once Daily in Four Clinical Studies
Study | No. of Patients | Treatment Group | EE Healing Rates |  | Significance Level [log-rank test vs. omeprazole 20 mg.]
Study | No. of Patients | Treatment Group | Week 4 | Week 8 | Significance Level [log-rank test vs. omeprazole 20 mg.]
1 | 588 | NEXIUM 20 mg | 68.7% | 90.6% | N.S.
1 | 588 | Omeprazole 20 mg | 69.5% | 88.3%
2 | 654 | NEXIUM 40 mg | 75.9% | 94.1% | p < 0.001
2 | 656 | NEXIUM 20 mg | 70.5% | 89.9% | p < 0.05
2 | 650 | Omeprazole 20 mg | 64.7% | 86.9%
3 | 576 | NEXIUM 40 mg | 71.5% | 92.2% | N.S.
3 | 572 | Omeprazole 20 mg | 68.6% | 89.8%
4 | 1216 | NEXIUM 40 mg | 81.7% | 93.7% | p < 0.001
4 | 1209 | Omeprazole 20 mg | 68.7% | 84.2%
N.S. = not significant (p > 0.05).

In these same studies of patients with EE, sustained heartburn resolution and time to sustained heartburn resolution were evaluated and are shown in Table 12:

Table 12: Sustained Resolution [Defined as 7 consecutive days with no heartburn reported in daily patient diary.] of Heartburn in Adults with EE Treated with NEXIUM Delayed-Release Capsules or Omeprazole Delayed-Release Capsules Once Daily in Four Clinical Studies
 |  |  | Cumulative Percent [Defined as the cumulative proportion of patients who have reached the start of sustained resolution.] with Sustained Resolution
Study | No. of Patients | Treatment Group | Day 14 | Day 28 | Significance Level [log-rank test vs. omeprazole 20 mg.]
1 | 573 | NEXIUM 20 mg | 64.3% | 72.7% | N.S.
 | 555 | Omeprazole 20 mg | 64.1% | 70.9%
2 | 621 | NEXIUM 40 mg | 64.8% | 74.2% | p <0.001
 | 620 | NEXIUM 20 mg | 62.9% | 70.1% | N.S.
 | 626 | Omeprazole 20 mg | 56.5% | 66.6%
3 | 568 | NEXIUM 40 mg | 65.4% | 73.9% | N.S.
 | 551 | Omeprazole 20 mg | 65.5% | 73.1%
4 | 1187 | NEXIUM 40 mg | 67.6% | 75.1% | p <0.001
 | 1188 | Omeprazole 20 mg | 62.5% | 70.8%
N.S. = not significant (p> 0.05)

In these four studies, the range of median days to the start of sustained resolution (defined as 7 consecutive days with no heartburn) was 5 days for NEXIUM 40 mg, 7 to 8 days for NEXIUM 20 mg and 7 to 9 days for omeprazole 20 mg.

There are no comparisons of 40 mg of NEXIUM with 40 mg of omeprazole in clinical trials assessing either healing or symptomatic relief of EE.

14.2 Maintenance of Healing of EE in Adults

Two multicenter, randomized, double-blind placebo-controlled 4-arm studies were conducted in adult patients with endoscopically confirmed, healed EE to evaluate NEXIUM delayed-release capsules 40 mg (n=174), 20 mg (n=180), 10 mg (n=168) or placebo (n=171) once daily over six months of treatment.

No additional clinical benefit was seen with NEXIUM 40 mg over NEXIUM 20 mg. NEXIUM 40 mg once daily is not a recommended regimen for the maintenance of healing of EE in adults.

The percentages of patients that maintained healing of EE at the various time points are shown in the Figures 2 and 3:

Figure 2: Maintenance of Healing Rates of EE in Adults by Month (Study 177)

s= scheduled visit

Figure 3: Maintenance of EE Healing Rates in Adults by Month (Study 178)

s= scheduled visit

Patients remained in remission significantly longer and the number of recurrences of EE was significantly less in patients treated with NEXIUM compared to placebo.

In both studies, the proportion of patients on NEXIUM who remained in remission and were free of heartburn and other GERD symptoms was well differentiated from placebo.

In a third multicenter open label study of 808 patients treated for 12 months with NEXIUM 40 mg, the percentage of patients that maintained healing of EE was 93.7% for six months and 89.4% for one year.

14.3 Symptomatic GERD in Adults

Two multicenter, randomized, double-blind, placebo-controlled studies were conducted in a total of 717 adult patients comparing four weeks of treatment with NEXIUM delayed-release capsules 20 mg or 40 mg once daily versus placebo for resolution of GERD symptoms. Patients had at least a 6-month history of heartburn episodes, no EE by endoscopy, and heartburn on at least four of the seven days immediately preceding randomization.

The percentage of patients that were symptom-free of heartburn was significantly higher in the NEXIUM groups compared to placebo at all follow-up visits (Weeks 1, 2, and 4).

No additional clinical benefit was seen with NEXIUM 40 mg over NEXIUM 20 mg. NEXIUM 40 mg once daily is not a recommended regimen for the treatment of symptomatic GERD in adults.

The percent of patients symptom-free of heartburn by day are shown in the Figures 4 and 5:

Figure 4: Percent of Patients Symptom-Free of Heartburn by Day (Study 225)

Figure 5: Percent of Patients Symptom-Free of Heartburn by Day (Study 226)

In three European symptomatic GERD trials, NEXIUM 20 mg and 40 mg and omeprazole 20 mg were evaluated. No significant treatment related differences were seen.

14.4 Pediatric GERD

1 Year to 11 Years of Age

In a multicenter, parallel-group study, 109 pediatric patients with a history of endoscopically-proven GERD (1 year to 11 years of age; 53 female; 89 Caucasian, 19 Black, 1 Other) were treated with NEXIUM for delayed-release oral suspension once daily for up to 8 weeks to evaluate safety and tolerability. Dosing by patient weight was as follows:

- weight < 20 kg: once daily treatment with NEXIUM for delayed-release oral suspension 5 mg or 10 mg
- weight ≥ 20 kg: once daily treatment with NEXIUM for delayed-release oral suspension 10 mg or 20 mg

Patients were endoscopically characterized as to the presence or absence of EE.

Of the 109 patients, 53 had EE at baseline (51 had mild, 1 moderate, and 1 severe esophagitis). Although most of the patients who had a follow up endoscopy at the end of 8 weeks of treatment healed, spontaneous healing cannot be ruled out because these patients had low grade EE prior to treatment, and the trial did not include a concomitant control.

12 Years to 17 Years of Age

In a multicenter, randomized, double-blind, parallel-group study, 149 adolescent patients (12 to 17 years of age; 89 female; 124 Caucasian, 15 Black, 10 Other) with clinically diagnosed GERD were treated with NEXIUM delayed-release capsules 20 mg or 40 mg once daily for up to 8 weeks to evaluate safety and tolerability. Patients were not endoscopically characterized as to the presence or absence of EE.

14.5 Risk Reduction of NSAID-Associated Gastric Ulcer

Two multicenter, double-blind, placebo-controlled studies were conducted in adult patients at risk of developing gastric and/or duodenal ulcers associated with continuous use of non-selective and COX-2 selective NSAIDs. A total of 1429 patients were randomized across the 2 studies. Patients ranged in age from 19 to 89 (median age 66 years) with 71% female, 29% male; 83% Caucasian, 5% Black, 4% Asian, and 8% Others. At baseline, the patients in these studies were endoscopically confirmed not to have ulcers but were determined to be at risk for ulcer occurrence due to their age (at least 60 years) and/or history of a documented gastric or duodenal ulcer within the past 5 years. Patients receiving NSAIDs and treated with NEXIUM delayed-release capsules 20 mg or 40 mg once daily experienced significant reduction in gastric ulcer occurrences relative to placebo treatment at 26 weeks. See Table 13. No additional benefit was seen with NEXIUM 40 mg over NEXIUM 20 mg. NEXIUM 40 mg once daily is not a recommended regimen for the risk reduction of NSAID-associated gastric ulcer in adults. These studies did not demonstrate significant reduction in the development of NSAID-associated duodenal ulcer due to the low incidence.

Table 13: Cumulative Percentage of Patients at Least 60 Years of Age Taking NSAIDS Without Gastric Ulcers at 26 Weeks in Two Randomized Placebo-Controlled Studies
Study | No. of Patients | Treatment Group | % of Patients Remaining Gastric Ulcer Free [%= Life Table Estimate. Significant difference from placebo (p<0.01).]
1 | 191; 194; 184 | NEXIUM 20 mg; NEXIUM 40 mg; Placebo | 95.4; 96.7; 88.2
2 | 267; 271; 257 | NEXIUM 20 mg; NEXIUM 40 mg; Placebo | 94.7; 95.3; 83.3

14.6 H. pylori Eradication in Adult Patients with Duodenal Ulcer Disease

Two multicenter, randomized, double-blind studies were conducted in adult patients using a 10-day treatment regimen of triple therapy (NEXIUM, amoxicillin and clarithromycin). The first study (191) compared NEXIUM delayed-release capsules 40 mg once daily in combination with amoxicillin 1000 mg twice daily and clarithromycin 500 mg twice daily to NEXIUM delayed-release capsules 40 mg once daily plus clarithromycin 500 mg twice daily. The second study (193) compared NEXIUM delayed-release capsules 40 mg once daily in combination with amoxicillin 1000 mg twice daily and clarithromycin 500 mg twice daily to NEXIUM delayed-release capsules 40 mg once daily. H. pylori eradication rates, defined as at least two negative tests and no positive tests from CLOtest®, histology and/or culture, at 4 weeks post-therapy were significantly higher in the NEXIUM, amoxicillin and clarithromycin group than in the NEXIUM and clarithromycin group or the NEXIUM alone group. The results are shown in Table 14:

Table 14: H. pylori Eradication Rates at 4 Weeks after 10 Day Treatment Regimen % of Adult Patients Cured [95% Confidence Interval] (Number of Patients)
Study | Treatment Group | Per-Protocol [Patients were included in the analysis if they had H. pylori infection documented at baseline, had at least one endoscopically verified duodenal ulcer ≥ 0.5 cm in diameter at baseline or had a documented history of duodenal ulcer disease within the past 5 years, and were not protocol violators. Patients who dropped out of the study due to an adverse reaction related to the study drug were included in the analysis as not H. pylori eradicated.] | Intent-to-Treat [Patients were included in the analysis if they had documented H. pylori infection at baseline, had at least one documented duodenal ulcer at baseline, or had a documented history of duodenal ulcer disease, and took at least one dose of study medication. All dropouts were included as not H. pylori eradicated.]
191 | NEXIUM, amoxicillin and clarithromycin | 84% [p < 0.05 compared to NEXIUM plus clarithromycin.]; [78, 89]; (n=196) | 77%; [71, 82]; (n=233)
 | NEXIUM and clarithromycin | 55%; [48, 62]; (n=187) | 52%; [45, 59]; (n=215)
193 | NEXIUM, amoxicillin and clarithromycin | 85% [p < 0.05 compared to NEXIUM alone.]; [74, 93]; (n=67) | 78%; [67, 87]; (n=74)
 | NEXIUM | 5%; [0, 23]; (n=22) | 4%; [0, 21]; (n=24)

The percentage of patients with a healed baseline duodenal ulcer by 4 weeks after the 10-day treatment regimen in the NEXIUM, amoxicillin and clarithromycin group was 75% (n=156) and 57% (n=60) respectively, in the 191 and 193 studies (per-protocol analysis).

14.7 Pathological Hypersecretory Conditions, Including Zollinger-Ellison Syndrome, in Adults

In a multicenter, open-label dose-escalation study of 21 adult patients (15 males and 6 females, 18 Caucasian and 3 Black, mean age of 56 years) with pathological hypersecretory conditions, such as Zollinger-Ellison Syndrome, NEXIUM significantly inhibited gastric acid secretion. The initial dosage of NEXIUM delayed-release capsules was 40 mg twice daily in 19 patients and 80 mg twice daily in 2 patients. Total daily doses ranging from 80 mg to 240 mg for 12 months maintained gastric acid output below the target levels of 10 mEq/h in patients without prior gastric acid-reducing surgery and below 5 mEq/hr in patients with prior gastric acid-reducing surgery. At the Month 12 final visit, 18/20 (90%) patients had Basal Acid Output (BAO) under satisfactory control (median BAO = 0.17 mmol/hr). Of the 18 patients evaluated with a starting dose of NEXIUM 40 mg twice daily, 13 (72%) had their BAO controlled with the original dosing regimen at the final visit. See Table 15.

Table 15: Adequate Acid Suppression at Final Visit by Dosage Regimen in Adult Patients with Pathological Hypersecretory Conditions
NEXIUM dose at the Month 12 visit | BAO under adequate control at the Month 12 visit (N=20) [One patient was not evaluated.]
40 mg twice daily | 13/15
80 mg twice daily | 4/4
80 mg three times daily | 1/1

16 HOW SUPPLIED/STORAGE AND HANDLING

NEXIUM Delayed-Release Capsules, 20 mg esomeprazole, are opaque, hard gelatin, amethyst colored capsules with two radial bars in yellow on the cap and NEXIUM 20 mg in yellow on the body. They are supplied as follows:

NDC 0186-5020-31 unit of use bottles of 30

NDC 0186-5020-54 bottles of 90

NEXIUM Delayed-Release Capsules, 40 mg esomeprazole, are opaque, hard gelatin, amethyst colored capsules with three radial bars in yellow on the cap and NEXIUM 40 mg in yellow on the body. They are supplied as follows:

NDC 0186-5040-31 unit of use bottles of 30

NDC 0186-5040-54 bottles of 90

NEXIUM For Delayed-Release Oral Suspension is supplied as a unit dose packet containing a fine yellow powder, consisting of white to pale brownish esomeprazole granules and pale yellow inactive granules. NEXIUM unit dose packets are supplied as follows:

NDC 0186-4025-01 unit dose packages of 30: 2.5 mg esomeprazole packets

NDC 0186-4050-01 unit dose packages of 30: 5 mg esomeprazole packets

NDC 0186-4010–01 unit dose packages of 30: 10 mg esomeprazole packets

NDC 0186-4020–01 unit dose packages of 30: 20 mg esomeprazole packets

NDC 0186-4040–01 unit dose packages of 30: 40 mg esomeprazole packets

Store at 25°C (77°F); excursions permitted to 15° to 30°C (59° to 86°F). [See USP Controlled Room Temperature]. Keep NEXIUM delayed-release capsules container tightly closed. Dispense in a tight container if the NEXIUM delayed-release capsules product package is subdivided.

17 PATIENT COUNSELING INFORMATION

Advise the patient to read the FDA-approved patient labeling (Medication Guide and Instructions for Use).

Acute Tubulointerstitial Nephritis

Advise the patient or caregiver to call the patient’s healthcare provider immediately if they experience signs and/or symptoms associated with suspected acute TIN [see Warnings and Precautions (5.2)].

Clostridium difficile-Associated Diarrhea

Advise the patient or caregiver to immediately call the patient’s healthcare provider if they experience diarrhea that does not improve [see Warnings and Precautions (5.3)].

Bone Fracture

Advise the patient or caregiver to report any fractures, especially of the hip, wrist or spine, to the patient’s healthcare provider [see Warnings and Precautions (5.4)].

Severe Cutaneous Adverse Reactions

Advise the patient or caregiver to discontinue NEXIUM and immediately call the patient’s healthcare provider for at first appearance of a severe cutaneous adverse reaction or other sign of hypersensitivity signs or symptoms associated with Severe Cutaneous Adverse Reactions [see Warnings and Precautions (5.5)].

Cutaneous and Systemic Lupus Erythematosus

Advise the patient or caregiver to immediately call the patient’s healthcare provider for any new or worsening of symptoms associated with cutaneous or systemic lupus erythematosus [see Warnings and Precautions (5.6)].

Cyanocobalamin (Vitamin B-12) Deficiency

Advise the patient or caregiver to report any clinical symptoms that may be associated with cyanocobalamin deficiency to the patient’s healthcare provider if they have been receiving NEXIUM for longer than 3 years [see Warnings and Precautions (5.8)].

Hypomagnesemia and Mineral Metabolism

Advise the patient or caregiver to report any clinical symptoms that may be associated with hypomagnesemia, hypocalcemia, and/or hypokalemia to the patient’s healthcare provider, if they have been receiving NEXIUM for at least 3 months [see Warnings and Precautions (5.9)].

Drug Interactions

Advise the patient or caregiver to report to their healthcare provider if starting treatment with rilpivirine-containing products, clopidogrel, St. John’s Wort or rifampin; or, if they take high-dose methotrexate [see Contraindications (4), Warnings and Precautions (5.7, 5.10, 5.12)].

Administration

- Take NEXIUM delayed-release capsules and NEXIUM for delayed-release oral suspension at least one hour before meals.
- Antacids may be used concomitantly with NEXIUM.
- Swallow NEXIUM delayed-release capsules whole; do not chew or crush the capsules.
- For patients who have difficulty swallowing capsules, NEXIUM delayed-release capsules can be opened, and the contents sprinkled on applesauce. Use with other foods is not recommended.
1. Add one tablespoon of applesauce to an empty bowl. The applesauce used should not be hot and should be soft enough to be swallowed without chewing.
2. Open the NEXIUM delayed-release capsule and carefully empty the granules inside the capsule onto the applesauce.
3. Mix the granules with the applesauce.
4. Administer the mixture immediately. Do not chew or crush the granules.
5. Discard any remaining mixture. Do not store the mixture for future use.
- NEXIUM delayed-release capsules can also be administered via a nasogastric tube, as described in the Instructions for Use.
- Administer NEXIUM for delayed-release oral suspension orally or via a nasogastric or gastric tube, as described in the Instructions for Use.

Distributed by:

AstraZeneca Pharmaceuticals LP

Wilmington, DE 19850

NEXIUM and the color purple as applied to the capsule are registered trademarks of the AstraZeneca group of companies.

©AstraZeneca 2023

MEDICATION GUIDE

NEXIUM® (nex-e-um) NEXIUM® (nex-e-um)

(esomeprazole magnesium) (esomeprazole magnesium)

delayed-release capsules, for oral use for delayed-release oral suspension

What is the most important information I should know about NEXIUM?

NEXIUM may help your acid-related symptoms, but you could still have serious stomach problems. Talk with your doctor.

NEXIUM can cause serious side effects, including:

- A type of kidney problem (acute tubulointerstitial nephritis). Some people who take proton pump inhibitor (PPI) medicines, including NEXIUM, may develop a kidney problem called acute tubulointerstitial nephritis that can happen at any time during treatment with NEXIUM. Call your doctor right away if you have a decrease in the amount that you urinate or if you have blood in your urine.
- Diarrhea caused by an infection (Clostridium difficile) in your intestines. Call your doctor right away if you have watery stools or stomach pain that does not go away. You may or may not have a fever.
- Bone fractures (hip, wrist, or spine). Bone fractures in the hip, wrist, or spine may happen in people who take multiple daily doses of PPI medicines and for a long period of time (a year or longer). Tell your doctor if you have a bone fracture, especially in the hip, wrist, or spine.
- Certain types of lupus erythematosus. Lupus erythematosus is an autoimmune disorder (the body’s immune cells attack other cells or organs in the body). Some people who take PPI medicines, including NEXIUM, may develop certain types of lupus erythematosus or have worsening of the lupus they already have. Call your doctor right away if you have new or worsening joint pain or a rash on your cheeks or arms that gets worse in the sun.

Talk to your doctor about your risk of these serious side effects.

NEXIUM can have other serious side effects. See “What are the possible side effects of NEXIUM?”

What is NEXIUM?

A prescription medicine called a proton pump inhibitor (PPI) used to reduce the amount of acid in your stomach.

NEXIUM is used in adults for:

- 4 to 8 weeks for the healing and symptom relief of acid-related damage to the esophagus (erosive esophagitis or EE). Your doctor may prescribe another 4-8 weeks of NEXIUM in patients whose EE does not heal.
- maintaining healing of EE.
- 4-8 weeks to treat heartburn and other symptoms that happen with gastroesophageal reflux disease (GERD).
- up to 6 months to reduce the risk of stomach ulcers in some people taking pain medicines called non-steroidal anti-inflammatory drugs (NSAIDs).
- treating patients with a stomach infection (Helicobacter pylori) and a stomach ulcer, along with the antibiotics amoxicillin and clarithromycin.
- the long-term treatment of conditions where your stomach makes too much acid, including Zollinger-Ellison Syndrome. Zollinger-Ellison Syndrome is a rare condition in which the stomach produces a more than normal amount of acid.

NEXIUM is used in children and adolescents 12 to 17 years of age for:

- 4 to 8 weeks to heal EE.
- 4 weeks to treat heartburn and other symptoms that happen with GERD.

NEXIUM is used in children 1 to 11 years of age for:

- 8 weeks to heal EE.
- up to 8 weeks to treat heartburn and other symptoms that happen with GERD.

NEXIUM is used in children 1 month to less than 1 year of age to treat GERD with EE for up to 6 weeks.

It is not known if NEXIUM is safe and effective in children under 1 month of age for the treatment of GERD with EE.

It is not known if NEXIUM is safe and effective in children less than 1 year of age for the treatment of GERD symptoms.

It is not known if NEXIUM is safe and effective in children to reduce the risk of stomach ulcers in children who take medicines called NSAIDs, to treat Helicobacter pylori stomach infection to lower the risk of a stomach ulcer returning, and to treat conditions where your stomach makes too much acid.

Do not take NEXIUM if you are:

- allergic to esomeprazole magnesium, any other PPI medicine, or any of the ingredients in NEXIUM. See the end of this Medication Guide for a complete list of ingredients in NEXIUM.

Tell your doctor right away or get emergency medical help if you get any of the following symptoms of an allergic reaction with NEXIUM:

  - rash
  - face swelling
  - throat tightness
  - difficulty breathing
- taking a medicine that contains rilpivirine (EDURANT, COMPLERA, ODEFSEY) used to treat HIV-1 (Human Immunodeficiency Virus).

Before taking NEXIUM, tell your doctor about all of your medical conditions, including if you:

- have low magnesium levels, low calcium levels and low potassium levels in your blood.
- have liver problems.
- are pregnant or plan to become pregnant. It is not known if NEXIUM will harm your unborn baby.
- are breastfeeding or planning to breastfeed. NEXIUM may pass into your breast milk. Talk to your doctor about the best way to feed your baby if you take NEXIUM.

Tell your doctor about all of the medicines you take, including prescription and over-the-counter medicines, vitamins, and herbal supplements.

Especially tell your doctor if you take: clopidogrel (Plavix), methotrexate (Otrxup, Rasuvo, Trexall, XATMEP), digoxin (LANOXIN), rilpivirine (EDURANT), St. John’s Wort (Hypericum perforatum), or rifampin (Rimactane, Rifater, Rifamate).

How should I take NEXIUM?

- Take NEXIUM exactly as prescribed by your doctor.
- Do not change your dose or stop NEXIUM without talking to your doctor.
- Take NEXIUM at least 1 hour before a meal.
- Antacids may be taken with NEXIUM.
- Swallow NEXIUM capsules whole. Never chew or crush NEXIUM.
- If you have difficulty swallowing NEXIUM capsules, you may open the capsule and empty the granules into 1 tablespoon of applesauce. The applesauce used should not be hot and should be soft enough to swallow without chewing. Do not mix the NEXIUM granules with any other food.
- Do not crush or chew the granules. Be sure to swallow the applesauce right away. Throw away any remaining mixture. Do not store it for later use.
- If you forget to take a dose of NEXIUM, take it as soon as you remember. If it is almost time for your next dose, do not take the missed dose. Take the next dose on time. Do not take a double dose to make up for a missed dose.
- If you take too much NEXIUM, call your doctor or local poison control center right away at 1-800-222-1222, or go to the nearest hospital emergency room.
- See the Instructions for Use at the end of this Medication Guide for instructions how to take NEXIUM for delayed-release oral suspension, and how to mix and give NEXIUM delayed-release capsules and NEXIUM for delayed-release oral suspension through a nasogastric tube or gastric tube.

What are the possible side effects of NEXIUM?

NEXIUM can cause serious side effects, including:

- See “What is the most important information I should know about NEXIUM?”
- Low vitamin B-12 levels in your body can happen in people who have taken NEXIUM for a long time (more than 3 years). Tell your doctor if you have symptoms of low vitamin B-12 levels, including shortness of breath, lightheadedness, irregular heartbeat, muscle weakness, pale skin, feeling tired, mood changes, and tingling or numbness in the arms and legs.
- Low magnesium levels in your body can happen in people who have taken NEXIUM for at least 3 months.
  Tell your doctor right away if you have symptoms of low magnesium levels, including seizures, dizziness, irregular heartbeat, jitteriness, muscle aches or weakness, and spasms of hands, feet or voice.
- Stomach growths (fundic gland polyps). People who take PPI medicines for a long time have an increased risk of developing a certain type of stomach growths called fundic gland polyps, especially after taking PPI medicines for more than 1 year.
- Severe skin reactions. NEXIUM can cause rare but severe skin reactions that may affect any part of your body. These serious skin reactions may need to be treated in a hospital and may be life threatening:
  - Skin rash which may have blistering, peeling or bleeding on any part of your skin (including your lips, eyes, mouth, nose, genitals, hands or feet).
  - You may also have fever, chills, body aches, shortness of breath, or enlarged lymph nodes.

Stop taking NEXIUM and call your doctor right away. These symptoms may be the first sign of a severe skin reaction.

The most common side effects of NEXIUM include:

- headache
- diarrhea
- nausea
- gas

- stomach (abdominal) pain
- constipation
- dry mouth

These are not all the possible side effects of NEXIUM.

Call your doctor for medical advice about side effects. You may report side effects to FDA at 1-800-FDA-1088.

How should I store NEXIUM?

- Store NEXIUM at room temperature between 68°F to 77°F (20°C to 25°C).
- Keep the container of NEXIUM closed tightly.

Keep NEXIUM and all medicines out of the reach of children.

General information about the safe and effective use of NEXIUM.

Medicines are sometimes prescribed for purposes other than those listed in a Medication Guide. Do not use NEXIUM for a condition for which it was not prescribed. Do not give NEXIUM to other people, even if they have the same symptoms you have. It may harm them.

You can ask your pharmacist or doctor for information about NEXIUM that is written for health professionals.

What are the ingredients in NEXIUM?

Active ingredient: esomeprazole magnesium trihydrate

Inactive ingredients in NEXIUM delayed-release capsules (including the capsule shells): glyceryl monostearate 40-55, hydroxypropyl cellulose, hypromellose, magnesium stearate, methacrylic acid copolymer type C, polysorbate 80, sugar spheres, talc, triethyl citrate, gelatin, FD&C Blue #1, FD&C Red #40, D&C Red #28, titanium dioxide, shellac, ethyl alcohol, isopropyl alcohol, n-butyl alcohol, propylene glycol, sodium hydroxide, polyvinyl pyrrolidone, and D&C Yellow #10.

Inactive granules in NEXIUM for delayed-release oral suspension: dextrose, xanthan gum, crospovidone, citric acid, iron oxide, and hydroxypropyl cellulose.

AstraZeneca Pharmaceuticals LP

Wilmington, DE 19850

NEXIUM is a registered trademark of the AstraZeneca group of companies.

©2020 AstraZeneca Pharmaceuticals LP. All rights reserved

For more information, go to www.purplepill.com or call 1-800-463-9486.

This Medication Guide has been approved by the U.S. Food and Drug Administration. Revised: March 2022

Instructions for Use

NEXIUM ® (nex-e-um)

(esomeprazole magnesium)

for delayed-release oral suspension

Taking NEXIUM in water:

- NEXIUM for delayed-release oral suspension comes in foil packets containing 2.5 mg, 5 mg, 10 mg, 20 mg, or 40 mg of NEXIUM.
- Use an oral syringe to measure the amount of water needed to mix your dose. Ask your pharmacist for an oral syringe.
- If your prescribed dose is 2.5 mg or 5 mg, add 5 mL of water to a container. Add the contents of a foil packet containing the dose prescribed by your doctor.
- If your prescribed dose is 10 mg, 20 mg, or 40 mg, add 15 mL of water to a container. Add the contents of a foil packet containing the dose prescribed by your doctor.
- If you or your child are instructed to use more than one foil packet for the prescribed dose, follow the mixing instructions provided by your pharmacist or doctor.
- Stir.
- Leave the mixture for 2 to 3 minutes to thicken.
- Stir and drink the mixture within 30 minutes. If not used within 30 minutes, throw away this dose and mix a new dose.
- If any medicine remains in the container after drinking, add more water, stir, and drink right away.
- For young children, you can give the dose with an oral syringe. Rinse the oral syringe with water after each use.

Giving NEXIUM with water through a nasogastric tube (NG tube) or gastric tube

NEXIUM delayed-release capsules:

- Open the capsule and empty the granules into a 60 mL catheter tipped syringe. Mix with 50 mL of water. Use only a catheter tipped syringe to give NEXIUM through a NG tube.
- Replace the plunger and shake the syringe well for 15 seconds. Hold the syringe with the tip up and check for granules in the tip.
- Do not give the granules if they have dissolved or have broken into pieces.
- Attach the syringe to the NG tube. Give the medicine right away in the syringe through the NG tube into the stomach.
- After giving the granules, flush the NG tube with more water.

NEXIUM for delayed-release oral suspension:

- NEXIUM for delayed-release oral suspension comes in foil packets containing 2.5 mg, 5 mg, 10 mg, 20 mg, or 40 mg of NEXIUM.
- Use only a catheter tipped syringe to give NEXIUM through a NG tube or gastric tube.
- If your prescribed dose is 2.5 mg or 5 mg, add 5 mL of water to a catheter tipped syringe. Add the contents of a foil packet containing the dose prescribed by your doctor.
- If your prescribed dose is 10 mg, 20 mg, or 40 mg, add 15 mL of water to a catheter tipped syringe. Add the contents of a foil packet containing the dose prescribed by your doctor.
- Shake the syringe well for 15 seconds and then leave it for 2 to 3 minutes to thicken.
- Shake the syringe and give the medicine through the NG or gastric tube (French size 6 or larger) into the stomach within 30 minutes.
- Refill the syringe with the same amount of water (either 5 mL or 15 mL of water depending on your dose).
- Shake the syringe and flush any remaining medicine from the NG tube or gastric tube into the stomach.

This Instructions for Use has been approved by the U.S. Food and Drug Administration.

AstraZeneca Pharmaceuticals LP

Wilmington, DE 19850

Revised 08/2021

NEXIUM is a registered trademark of the AstraZeneca group of companies.

©2020 AstraZeneca Pharmaceuticals LP. All rights reserved

PACKAGE/LABEL PRINCIPAL DISPLAY PANEL – 20 mg 30 Capsules

NDC 0186-5020-31

NEXIUM®

(esomeprazole magnesium)

30 Delayed-Release

Capsules

Rx only 20 mg*

Dispense the accompanying

Medication Guide to each patient.

AstraZeneca

PACKAGE/LABEL PRINCIPAL DISPLAY PANEL – 40 mg 30 Capsules

NDC 0186-5040-31

NEXIUM®

(esomeprazole magnesium)

30 Delayed-Release

Capsules

Rx only 40 mg*

Dispense the accompanying

Medication Guide to each patient.

AstraZeneca

PACKAGE/LABEL PRINCIPAL DISPLAY PANEL – 2.5 mg Oral Suspension

NDC 0186-4025-01

NEXIUM®

(esomeprazole magnesium*)

2.5 mg

For Delayed-Release Oral Suspension

Each carton contains 30 child-resistant packets.

*Each packet of delayed release oral suspension contains 2.5 mg of esomeprazole (equivalent to 2.8 mg of esomeprazole magnesium trihydrate).

Dispense the enclosed Medication Guide to each patient.

30 Single Dose Packets

Rx only

AstraZeneca

PACKAGE/LABEL PRINCIPAL DISPLAY PANEL – 5 mg Oral Suspension

NDC 0186-4050-01

NEXIUM®

(esomeprazole magnesium*)

5 mg

For Delayed-Release

Oral Suspension

Each carton contains 30 child-resistant packets.

*Each packet of delayed release oral suspension contains 5 mg of esomeprazole (equivalent to 5.6 mg of esomeprazole magnesium trihydrate).

Dispense the enclosed Medication Guide to each patient.

Rx only

30 Single Dose Packets

AstraZeneca

PACKAGE/LABEL PRINCIPAL DISPLAY PANEL – 10 mg Oral Suspension

NDC 0186-4010-01

NEXIUM®

(esomeprazole magnesium*)

10 mg

For Delayed-Release

Oral Suspension

Each carton contains 30 child-resistant packets.

*Each packet of delayed release oral suspension contains 10 mg of esomeprazole (equivalent to 11.1 mg of esomeprazole magnesium trihydrate).

Dispense the enclosed Medication Guide to each patient.

Rx only

30 Single Dose Packets

AstraZeneca

PACKAGE/LABEL PRINCIPAL DISPLAY PANEL – 20 mg Oral Suspension

NDC 0186-4020-01

NEXIUM®

(esomeprazole magnesium*)

20 mg

For Delayed-Release

Oral Suspension

Each carton contains 30 child-resistant packets.

*Each packet of delayed release oral suspension contains 20 mg of esomeprazole (equivalent to 22.3 mg of esomeprazole magnesium trihydrate).

Dispense the enclosed Medication Guide to each patient.

Rx only

30 Single Dose Packets

AstraZeneca

Package/Label Display Panel

NDC 0186-4040-01

NEXIUM®

(esomeprazole magnesium*)

40 mg

For Delayed-Release Oral Suspension

Each carton contains 30 child-resistant packets.

*Each packet of delayed release oral suspension contains 40 mg of esomeprazole (equivalent to 44.5 mg of esomeprazole magnesium trihydrate).

Dispense the enclosed Medication Guide to each patient.

Rx only

30 Single Dose Packets

AstraZeneca